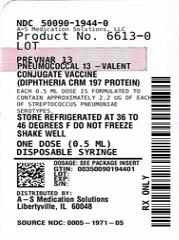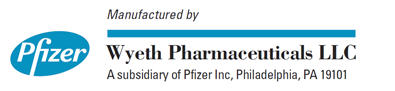 DRUG LABEL: PREVNAR 13
NDC: 50090-1944 | Form: INJECTION, SUSPENSION
Manufacturer: A-S Medication Solutions
Category: other | Type: VACCINE LABEL
Date: 20240524

ACTIVE INGREDIENTS: STREPTOCOCCUS PNEUMONIAE TYPE 1 CAPSULAR POLYSACCHARIDE DIPHTHERIA CRM197 PROTEIN CONJUGATE ANTIGEN 2.2 ug/0.5 mL; STREPTOCOCCUS PNEUMONIAE TYPE 3 CAPSULAR POLYSACCHARIDE DIPHTHERIA CRM197 PROTEIN CONJUGATE ANTIGEN 2.2 ug/0.5 mL; STREPTOCOCCUS PNEUMONIAE TYPE 4 CAPSULAR POLYSACCHARIDE DIPHTHERIA CRM197 PROTEIN CONJUGATE ANTIGEN 2.2 ug/0.5 mL; STREPTOCOCCUS PNEUMONIAE TYPE 5 CAPSULAR POLYSACCHARIDE DIPHTHERIA CRM197 PROTEIN CONJUGATE ANTIGEN 2.2 ug/0.5 mL; STREPTOCOCCUS PNEUMONIAE TYPE 6A CAPSULAR POLYSACCHARIDE DIPHTHERIA CRM197 PROTEIN CONJUGATE ANTIGEN 2.2 ug/0.5 mL; STREPTOCOCCUS PNEUMONIAE TYPE 6B CAPSULAR POLYSACCHARIDE DIPHTHERIA CRM197 PROTEIN CONJUGATE ANTIGEN 4.4 ug/0.5 mL; STREPTOCOCCUS PNEUMONIAE TYPE 7F CAPSULAR POLYSACCHARIDE DIPHTHERIA CRM197 PROTEIN CONJUGATE ANTIGEN 2.2 ug/0.5 mL; STREPTOCOCCUS PNEUMONIAE TYPE 9V CAPSULAR POLYSACCHARIDE DIPHTHERIA CRM197 PROTEIN CONJUGATE ANTIGEN 2.2 ug/0.5 mL; STREPTOCOCCUS PNEUMONIAE TYPE 14 CAPSULAR POLYSACCHARIDE DIPHTHERIA CRM197 PROTEIN CONJUGATE ANTIGEN 2.2 ug/0.5 mL; STREPTOCOCCUS PNEUMONIAE TYPE 18C CAPSULAR POLYSACCHARIDE DIPHTHERIA CRM197 PROTEIN CONJUGATE ANTIGEN 2.2 ug/0.5 mL; STREPTOCOCCUS PNEUMONIAE TYPE 23F CAPSULAR POLYSACCHARIDE DIPHTHERIA CRM197 PROTEIN CONJUGATE ANTIGEN 2.2 ug/0.5 mL; STREPTOCOCCUS PNEUMONIAE TYPE 19A CAPSULAR POLYSACCHARIDE DIPHTHERIA CRM197 PROTEIN CONJUGATE ANTIGEN 2.2 ug/0.5 mL; STREPTOCOCCUS PNEUMONIAE TYPE 19F CAPSULAR POLYSACCHARIDE DIPHTHERIA CRM197 PROTEIN CONJUGATE ANTIGEN 2.2 ug/0.5 mL
INACTIVE INGREDIENTS: CORYNEBACTERIUM DIPHTHERIAE CRM197 PROTEIN 34 ug/0.5 mL; POLYSORBATE 80 100 ug/0.5 mL; ALUMINUM PHOSPHATE 125 ug/0.5 mL; SUCCINATE DIANION 295 ug/0.5 mL

HIGHLIGHTS OF PRESCRIBING INFORMATION

These highlights do not include all the information needed to use PREVNAR 13 safely and effectively. See full prescribing information for PREVNAR 13.
PREVNAR 13 (Pneumococcal 13-valent Conjugate Vaccine
[Diphtheria CRM197 Protein])
Suspension for intramuscular injection
Initial U.S. Approval: 2010

1 INDICATIONS AND USAGE

In children 6 weeks through 5 years of age (prior to the 6th birthday), Prevnar 13 is indicated for:

- active immunization for the prevention of invasive disease caused by Streptococcus pneumoniae serotypes 1, 3, 4, 5, 6A, 6B, 7F, 9V, 14, 18C, 19A, 19F and 23F. (1.1)
- active immunization for the prevention of otitis media caused by S. pneumoniae serotypes 4, 6B, 9V, 14, 18C, 19F, and 23F. No otitis media efficacy data are available for serotypes 1, 3, 5, 6A, 7F, and 19A. (1.1)

In children 6 years through 17 years of age (prior to the 18th birthday), Prevnar 13 is indicated for:

- active immunization for the prevention of invasive disease caused by S. pneumoniae serotypes 1, 3, 4, 5, 6A, 6B, 7F, 9V, 14, 18C, 19A, 19F and 23F. (1.2)

In adults 18 years of age and older, Prevnar 13 is indicated for:

- active immunization for the prevention of pneumonia and invasive disease caused by S. pneumoniae serotypes 1, 3, 4, 5, 6A, 6B, 7F, 9V, 14, 18C, 19A, 19F and 23F. (1.3)

Limitations of Prevnar 13 Use and Effectiveness

- Prevnar 13 does not protect against disease caused by S. pneumoniae serotypes that are not in the vaccine. (1.4)

2 DOSAGE AND ADMINISTRATION

Children 6 weeks through 5 years: The four-dose immunization series consists of a 0.5 mL intramuscular injection administered at 2, 4, 6, and 12–15 months of age. (2.3)

Children 6 through 17 years of age: a single dose. (2.5)

Adults 18 years and older: a single dose. (2.6)

3 DOSAGE FORMS AND STRENGTHS

0.5 mL suspension for intramuscular injection, supplied in a single-dose prefilled syringe. (3)

4 CONTRAINDICATIONS

Severe allergic reaction (e.g., anaphylaxis) to any component of Prevnar 13 or any diphtheria toxoid-containing vaccine. (4)

5 WARNINGS AND PRECAUTIONS

Apnea following intramuscular vaccination has been observed in some infants born prematurely. Decisions about when to administer an intramuscular vaccine, including Prevnar 13, to infants born prematurely should be based on consideration of the individual infant's medical status, and the potential benefits and possible risks of vaccination. (5.3)

6 ADVERSE REACTIONS

- In infants and toddlers vaccinated at 2, 4, 6, and 12–15 months of age in US clinical trials, the most commonly reported solicited adverse reactions (>5%) were irritability (>70%), injection site tenderness (>50%), decreased appetite (>40%), decreased sleep (>40%), increased sleep (>40%), fever (>20%), injection site redness (>20%), and injection site swelling (>20%). (6.1)
- In children aged 5 through 17 years, the most commonly reported solicited adverse reactions (>5%) were injection site tenderness (>80%), injection site redness (>30%), injection site swelling (>30%), irritability (>20%), decreased appetite (>20%), increased sleep (>20%), fever (>5%), and decreased sleep (>5%). (6.1)
- In adults aged 18 years and older, the most commonly reported solicited adverse reactions (>5%) were pain at the injection site (>50%), fatigue (>30%), headache (>20%), muscle pain (>20%), joint pain (>10%), decreased appetite (>10%), injection site redness (>10%), injection site swelling (>10%), limitation of arm movement (>10%), vomiting (>5%), fever (>5%), chills (>5%), and rash (>5%). (6.2)

To report SUSPECTED ADVERSE REACTIONS, contact Wyeth Pharmaceuticals LLC. at 1-800-438-1985 or VAERS at 1-800-822-7967 or http://vaers.hhs.gov.

8 USE IN SPECIFIC POPULATIONS

Pediatric Use: Safety and effectiveness of Prevnar 13 in children below the age of 6 weeks have not been established. (8.4)

FULL PRESCRIBING INFORMATION

1 INDICATIONS AND USAGE

1.1 Children 6 Weeks Through 5 Years of Age

In children 6 weeks through 5 years of age (prior to the 6th birthday), Prevnar 13® is indicated for:

- active immunization for the prevention of invasive disease caused by Streptococcus pneumoniae serotypes 1, 3, 4, 5, 6A, 6B, 7F, 9V, 14, 18C, 19A, 19F and 23F.
- active immunization for the prevention of otitis media caused by S. pneumoniae serotypes 4, 6B, 9V, 14, 18C, 19F, and 23F. No otitis media efficacy data are available for serotypes 1, 3, 5, 6A, 7F, and 19A.

1.2 Children 6 Years Through 17 Years of Age

In children 6 years through 17 years of age (prior to the 18th birthday), Prevnar 13 is indicated for:

- active immunization for the prevention of invasive disease caused by S. pneumoniae serotypes 1, 3, 4, 5, 6A, 6B, 7F, 9V, 14, 18C, 19A, 19F and 23F.

1.3 Adults 18 Years of Age and Older

In adults 18 years of age and older, Prevnar 13 is indicated for:
2. active immunization for the prevention of pneumonia and invasive disease caused by S. pneumoniae serotypes 1, 3, 4, 5, 6A, 6B, 7F, 9V, 14, 18C, 19A, 19F and 23F.

1.4 Limitations of Prevnar 13 Use and Effectiveness

- Prevnar 13 does not protect against disease caused by S. pneumoniae serotypes that are not in the vaccine.

2 DOSAGE AND ADMINISTRATION

2.1 Preparation for Administration

Since this product is a suspension containing an adjuvant, shake vigorously immediately prior to use to obtain a homogenous, white suspension in the vaccine container. Do not use the vaccine if it cannot be resuspended. Parenteral drug products should be inspected visually for particulate matter and discoloration prior to administration [see Description (11)]. This product should not be used if particulate matter or discoloration is found.

Do not mix Prevnar 13 with other vaccines/products in the same syringe.

2.2 Administration Information

For intramuscular injection only.

Each 0.5 mL dose is to be injected intramuscularly using a sterile needle attached to the supplied prefilled syringe. The preferred sites for injection are the anterolateral aspect of the thigh in infants and the deltoid muscle of the upper arm in toddlers, children and adults. The vaccine should not be injected in the gluteal area or areas where there may be a major nerve trunk and/or blood vessel.

2.3 Vaccination Schedule for Infants and Toddlers

Prevnar 13 is to be administered as a four-dose series at 2, 4, 6, and 12–15 months of age.

Table 1: Vaccination Schedule for Infants and Toddlers
Dose | Dose 1 [Dose 1 may be given as early as 6 weeks of age.] , [The recommended dosing interval is 4 to 8 weeks.] | Dose 2 | Dose 3 | Dose 4 [The fourth dose should be administered at approximately 12–15 months of age, and at least 2 months after the third dose.]
Age at Dose | 2 months | 4 months | 6 months | 12–15 months

2.4 Vaccination Schedule for Unvaccinated Children 7 Months Through 5 Years of Age

For children 7 months through 5 years of age who have not received Prevnar® or Prevnar 13, the catch-up schedule in Table 2 applies:

Table 2: Vaccination Schedule for Unvaccinated Children 7 Months of Age Through 5 Years of Age
Age at First Dose | Total Number of 0.5 mL Doses
7–11 months of age | 3 [The first 2 doses at least 4 weeks apart; third dose after the one-year birthday, separated from the second dose by at least 2 months.]
12–23 months of age | 2 [Two doses at least 2 months apart.]
24 months through 5 years of age (prior to the 6th birthday) | 1

The immune responses induced by this catch-up schedule may result in lower antibody concentrations for some serotypes, compared to antibody concentrations following 4 doses of Prevnar 13 (given at 2, 4, 6, and 12–15 months). In children 24 months through 5 years of age, lower antibody concentrations were observed for some serotypes, compared to antibody concentrations following 3 doses of Prevnar 13 (given at 2, 4, and 6 months).

2.5 Vaccination Schedule for Children 6 Years Through 17 Years of Age

In children 6 years through 17 years of age, Prevnar 13 is administered as single dose. If Prevnar was previously administered, then at least 8 weeks should elapse before receiving Prevnar 13.

2.6 Vaccination Schedule for Adults 18 Years of Age and Older

Prevnar 13 is administered as a single dose.

3 DOSAGE FORMS AND STRENGTHS

Prevnar 13 is a suspension for intramuscular injection available in 0.5 mL single-dose prefilled syringes.

4 CONTRAINDICATIONS

Severe allergic reaction (e.g., anaphylaxis) to any component of Prevnar 13 or any diphtheria toxoid-containing vaccine [see Description (11)].

5 WARNINGS AND PRECAUTIONS

5.1 Management of Allergic Reactions

Epinephrine and other appropriate agents used to manage immediate allergic reactions must be immediately available should an acute anaphylactic reaction occur following administration of Prevnar 13.

5.2 Altered Immunocompetence

Individuals with altered immunocompetence, including those at higher risk for invasive pneumococcal disease (e.g., individuals with congenital or acquired splenic dysfunction, HIV infection, malignancy, hematopoietic stem cell transplant, nephrotic syndrome), may have reduced antibody responses to immunization with Prevnar 13 [see Use in Specific Populations (8.6)].

5.3 Apnea in Premature Infants

Apnea following intramuscular vaccination has been observed in some infants born prematurely. Decisions about when to administer an intramuscular vaccine, including Prevnar 13, to infants born prematurely should be based on consideration of the individual infant's medical status and the potential benefits and possible risks of vaccination.

6 ADVERSE REACTIONS

Because clinical trials are conducted under widely varying conditions, adverse-reaction rates observed in the clinical trials of a vaccine cannot be directly compared to rates in the clinical trials of another vaccine and may not reflect the rates observed in practice.

6.1 Clinical Trials Experience With Prevnar 13 in Children 6 Weeks Through 17 Years of Age

The safety of Prevnar 13 was evaluated in 13 clinical trials in which 4,729 infants (6 weeks through 11 months of age) and toddlers (12 months through 15 months of age) received at least one dose of Prevnar 13 and 2,760 infants and toddlers received at least one dose of Prevnar active control. Safety data for the first three doses are available for all 13 infant studies; dose 4 data are available for 10 studies; and data for the 6-month follow-up are available for 7 studies. The vaccination schedule and concomitant vaccinations used in these infant trials were consistent with country-specific recommendations and local clinical practice. There were no substantive differences in demographic characteristics between the vaccine groups. By race, 84.0% of subjects were White, 6.0% were Black or African-American, 5.8% were Asian and 3.8% were of 'Other' race (most of these being biracial). Overall, 52.3% of subjects were male infants.

Three studies in the US (Studies 1, 2 and 3)^1,2,3 evaluated the safety of Prevnar 13 when administered concomitantly with routine US pediatric vaccinations at 2, 4, 6, and 12–15 months of age. Solicited local and systemic adverse reactions were recorded daily by parents/guardians using an electronic diary for 7 consecutive days following each vaccination. For unsolicited adverse events, study subjects were monitored from administration of the first dose until one month after the infant series, and for one month after the administration of the toddler dose. Information regarding unsolicited and serious adverse events, newly diagnosed chronic medical conditions, and hospitalizations since the last visit were collected during the clinic visit for the fourth-study dose and during a scripted telephone interview 6 months after the fourth-study dose. Serious adverse events were also collected throughout the study period. Overall, the safety data show a similar proportion of Prevnar 13 and Prevnar subjects reporting serious adverse events. Among US study subjects, a similar proportion of Prevnar 13 and Prevnar recipients reported solicited local and systemic adverse reactions as well as unsolicited adverse events.

Serious Adverse Events in All Infant and Toddler Clinical Studies

Serious adverse events were collected throughout the study period for all 13 clinical trials. This reporting period is longer than the 30-day post-vaccination period used in some vaccine trials. The longer reporting period may have resulted in serious adverse events being reported in a higher percentage of subjects than for other vaccines. Serious adverse events reported following vaccination in infants and toddlers occurred in 8.2% among Prevnar 13 recipients and 7.2% among Prevnar recipients. Serious adverse events observed during different study periods for Prevnar 13 and Prevnar respectively were: 1) 3.7% and 3.5% from dose 1 to the blood draw approximately 1 month after the infant series; 2) 3.6% and 2.7% from the blood draw after the infant series to the toddler dose; 3) 0.9% and 0.8% from the toddler dose to the blood draw approximately 1 month after the toddler dose and 4) 2.5% and 2.8% during the 6 month follow-up period after the last dose.

The most commonly reported serious adverse events were in the 'Infections and infestations' system organ class including bronchiolitis (0.9%, 1.1%), gastroenteritis, (0.9%, 0.9%), and pneumonia (0.9%, 0.5%) for Prevnar 13 and Prevnar respectively.

There were 3 (0.063%) deaths among Prevnar 13 recipients, and 1 (0.036%) death in Prevnar recipients, all as a result of sudden infant death syndrome (SIDS). These SIDS rates are consistent with published age specific background rates of SIDS from the year 2000.

Among 6,839 subjects who received at least 1 dose of Prevnar 13 in clinical trials conducted globally, there was 1 hypotonic-hyporesponsive episode adverse reaction reported (0.015%). Among 4,204 subjects who received at least 1 dose of Prevnar in clinical trials conducted globally, there were 3 hypotonic-hyporesponsive episode adverse reactions reported (0.071%). All 4 events occurred in a single clinical trial in Brazil in which subjects received whole cell pertussis vaccine at the same time as Prevnar 13 or Prevnar.

Solicited Adverse Reactions in the Three US Infant and Toddler Studies

A total of 1,907 subjects received at least 1 dose of Prevnar 13 and 701 subjects received at least 1 dose of Prevnar in the three US studies (Studies 1, 2 and 3)^1,2,3. Most subjects were White (77.3%), 14.2% were Black or African-American, and 1.7% were Asian; 79.1% of subjects were non-Hispanic and non-Latino and 14.6% were Hispanic or Latino. Overall, 53.6% of subjects were male infants.

The incidence and severity of solicited adverse reactions that occurred within 7 days following each dose of Prevnar 13 or Prevnar administered to US infants and toddlers are shown in Tables 3 and 4.

Table 3: Percentage of US Infant and Toddler Subjects Reporting Solicited Local Reactions at the Prevnar 13 or Prevnar Injection Sites Within 7 Days After Each Vaccination at 2, 4, 6, and 12–15 Months of Age [Data are from three primary US safety studies (the US Phase 2 infant study [National Clinical Trial (NCT) number NCT00205803] Study 1, the US noninferiority study [NCT00373958] Study 2, and the US lot consistency study [NCT00444457] Study 3). All infants received concomitant routine infant immunizations. Concomitant vaccines and pneumococcal conjugate vaccines were administered in different limbs.]
 | Dose 1 |  | Dose 2 |  | Dose 3 |  | Dose 4
Graded Local Reaction | Prevnar 13 (N [Number of subjects reporting Yes for at least 1 day or No for all days.] =1375–1612) % | Prevnar (N=516–606) % | Prevnar 13 (N=1069–1331) % | Prevnar (N=405–510) % | Prevnar 13 (N=998–1206) % | Prevnar (N=348–446) % | Prevnar 13 (N=874–1060) % | Prevnar (N=283–379) %
Redness [Diameters were measured in caliper units of whole numbers from 1 to 14 or 14+. One caliper unit = 0.5 cm. Measurements were rounded up to the nearest whole number. Intensity of induration and erythema were then characterized as Mild (0.5–2.0 cm), Moderate (2.5–7.0 cm), or Severe (>7.0 cm).]
Any | 24.3 | 26.0 | 33.3 | 29.7 | 37.1 | 36.6 | 42.3 | 45.5
Mild | 23.1 | 25.2 | 31.9 | 28.7 | 35.3 | 35.3 | 39.5 | 42.7
Moderate | 2.2 | 1.5 | 2.7 | 2.2 | 4.6 | 5.1 | 9.6 | 13.4 [Statistically significant difference p <0.05. No adjustments for multiplicity.]
Severe | 0 | 0 | 0 | 0 | 0 | 0 | 0 | 0
Swelling
Any | 20.1 | 20.7 | 25.2 | 22.5 | 26.8 | 28.4 | 31.6 | 36.0
Mild | 17.2 | 18.7 | 23.8 | 20.5 | 25.2 | 27.5 | 29.4 | 33.8
Moderate | 4.9 | 3.9 | 3.7 | 4.9 | 3.8 | 5.8 | 8.3 | 11.2
Severe | 0 | 0 | 0.1 | 0 | 0 | 0 | 0 | 0
Tenderness
Any | 62.5 | 64.5 | 64.7 | 62.9 | 59.2 | 60.8 | 57.8 | 62.5
Interferes with limb movement | 10.4 | 9.6 | 9.0 | 10.5 | 8.4 | 9.0 | 6.9 | 5.7

Table 4: Percentage of US Infant and Toddler Subjects Reporting Solicited Systemic Adverse Reactions Within 7 Days After Each Vaccination at 2, 4, 6, and 12–15 Months of Age [Number of subjects reporting Yes for at least 1 day or No for all days.] , [Data are from three primary US safety studies (the US Phase 2 infant study [NCT00205803] Study 1, the US noninferiority study [NCT00373958] Study 2, and the US lot consistency study [NCT00444457] Study 3). All infants received concomitant routine infant immunizations. Concomitant vaccines and pneumococcal conjugate vaccines were administered in different limbs.]
 | Dose 1 |  | Dose 2 |  | Dose 3 |  | Dose 4
Graded Systemic Events | Prevnar 13 (N=1360 – 1707) % | Prevnar (N=497–640) % | Prevnar 13 (N=1084–1469) % | Prevnar (N=409–555) % | Prevnar 13 (N=997–1361) % | Prevnar (N=354–521) % | Prevnar 13 (N=850–1227) % | Prevnar (N=278–436) %
Fever [Fever gradings: Mild (≥38°C but ≤39°C), Moderate (>39°C but ≤40°C), and Severe (>40°C). No other systemic event other than fever was graded. Parents reported the use of antipyretic medication to treat or prevent symptoms in 62 to 75% of subjects after any of the 4 doses. There were no statistical differences in frequencies of adverse reactions reported between the Prevnar 13 and Prevnar groups.]
Any | 24.3 | 22.1 | 36.5 | 32.8 | 30.3 | 31.6 | 31.9 | 30.6
Mild | 23.6 | 21.7 | 34.9 | 31.6 | 29.1 | 30.2 | 30.3 | 30.0
Moderate | 1.1 | 0.6 | 3.4 | 2.8 | 4.2 | 3.3 | 4.4 | 4.6
Severe | 0.1 | 0.2 | 0.1 | 0.3 | 0.1 | 0.7 | 1.0 | 0
Decreased appetite | 48.3 | 43.6 | 47.8 | 43.6 | 47.6 | 47.6 | 51.0 | 49.4
Irritability | 85.6 | 83.6 | 84.8 | 80.4 | 79.8 | 80.8 | 80.4 | 77.8
Increased sleep | 71.5 | 71.5 | 66.6 | 63.4 | 57.7 | 55.2 | 48.7 | 55.1
Decreased sleep | 42.5 | 40.6 | 45.6 | 43.7 | 46.5 | 47.7 | 45.3 | 40.3

The incidence rates of any fever (≥38.0°C) were similar on days 1 and 2 following each dose of Prevnar 13 compared to after each dose of Prevnar administered to US infants and toddlers (day 1 = day of vaccination). After dose 1, fever was reported in 11.0–12.7% on day 1 and 6.4–6.8% on day 2. After dose 2, fever was reported in 12.3–13.1% on day 1 and 12.5–12.8% on day 2. After dose 3, fever was reported in 8.0–9.6% on day 1 and 9.1–10.5% on day 2. And after dose 4, fever was reported in 6.3–6.4% on day 1 and 7.3–9.7% on day 2.

Unsolicited Adverse Reactions in the Three US Infant and Toddler Safety Studies

The following were determined to be adverse drug reactions based on experience with Prevnar 13 in clinical trials.

Reactions occurring in greater than 1% of infants and toddlers: diarrhea, vomiting, and rash.

Reactions occurring in less than 1% of infants and toddlers: crying, hypersensitivity reaction (including face edema, dyspnea, and bronchospasm), seizures (including febrile seizures), and urticaria or urticaria-like rash.

Safety Assessments in the Catch-Up Studies in Infants and Children Through 5 Years of Age

In a catch-up study^4 conducted in Poland (Study 4), 354 children (7 months through 5 years of age) receiving at least one dose of Prevnar 13 were also monitored for safety. All subjects in this study were White and non-Hispanic. Overall, 49.6% of subjects were male infants. The incidence and severity of solicited adverse reactions that occurred within 4 days following each dose of Prevnar 13 administered to pneumococcal-vaccine naïve children 7 months through 5 years of age are shown in Tables 5 and 6.

Table 5: Percentage of Subjects 7 Months Through 5 Years of Age Reporting Solicited Local Reactions Within 4 Days After Each Catch-Up Prevnar 13 Vaccination [Study conducted in Poland (NCT00452452) Study 4.]
 | 7 through 11 months |  |  | 12 through 23 months |  | 24 months through 5 years
Graded Local Reaction | Dose 1 N [Number of subjects reporting Yes for at least 1 day or No for all days.] =86 % | Dose 2 N=86–87 % | Dose 3 N=78–82 % | Dose 1 N=108–110 % | Dose 2 N=98–106 % | Dose 1 N=147–149 %
Redness [Diameters were measured in caliper units of whole numbers from 1 to 14 or 14+. One caliper unit = 0.5 cm. Measurements were rounded up to the nearest whole number. Intensity of redness and swelling were then characterized as Mild (0.5–2.0 cm), Moderate (2.5–7.0 cm), or Severe (>7.0 cm).]
Any | 48.8 | 46.0 | 37.8 | 70.0 | 54.7 | 50.0
Mild | 41.9 | 40.2 | 31.3 | 55.5 | 44.7 | 37.4
Moderate | 16.3 | 9.3 | 12.5 | 38.2 | 25.5 | 25.7
Severe | 0.0 | 0.0 | 0.0 | 0.0 | 0.0 | 0.0
Swelling
Any | 36.0 | 32.2 | 25.0 | 44.5 | 41.0 | 36.9
Mild | 32.6 | 28.7 | 20.5 | 36.7 | 36.2 | 28.2
Moderate | 11.6 | 14.0 | 11.3 | 24.8 | 12.1 | 20.3
Severe | 0.0 | 0.0 | 0.0 | 0.0 | 0.0 | 0.0
Tenderness
Any | 15.1 | 15.1 | 15.2 | 33.3 | 43.7 | 42.3
Interferes with limb movement | 1.2 | 3.5 | 6.4 | 0.0 | 4.1 | 4.1

Table 6: Percentage of Subjects 7 Months Through 5 Years of Age Reporting Solicited Systemic Adverse Reactions Within 4 Days After Each Catch-Up Prevnar 13 Vaccination [Study conducted in Poland (NCT00452452) Study 4.]
 | 7 through 11 months |  |  | 12 through 23 months |  | 24 months through 5 years
Systemic Reaction | Dose 1 N [Number of subjects reporting Yes for at least 1 day or No for all days.] =86–87 % | Dose 2 N=86–87 % | Dose 3 N=78–81 % | Dose 1 N=108 % | Dose 2 N=98–100 % | Dose 1 N=147–148 %
Fever [Fever gradings: Mild (≥38°C but ≤39°C), Moderate (>39°C but ≤40°C), and Severe (>40°C). No other systemic event other than fever was graded.]
Mild | 3.4 | 8.1 | 5.1 | 3.7 | 5.1 | 0.7
Moderate | 1.2 | 2.3 | 1.3 | 0.9 | 0.0 | 0.7
Severe | 0.0 | 0.0 | 0.0 | 0.0 | 0.0 | 0.0
Decreased appetite | 19.5 | 17.2 | 17.5 | 22.2 | 25.5 | 16.3
Irritability | 24.1 | 34.5 | 24.7 | 30.6 | 34.0 | 14.3
Increased sleep | 9.2 | 9.3 | 2.6 | 13.0 | 10.1 | 11.6
Decreased sleep | 24.1 | 18.4 | 15.0 | 19.4 | 20.4 | 6.8

A US study^5 (Study 5) evaluated the use of Prevnar 13 in children previously immunized with Prevnar. In this open label trial, 596 healthy children 15 through 59 months of age previously vaccinated with at least 3 doses of Prevnar, received 1 or 2 doses of Prevnar 13. Children 15 months through 23 months of age (group 1) received 2 doses, and children 24 months through 59 months of age (group 2) received one dose. Most subjects were White (74.3%), 14.9% were Black or African-American, and 1.2% were Asian; 89.3% of subjects were non-Hispanic and non-Latino and 10.7% were Hispanic or Latino. Overall, 52.2% of subjects were male.

The incidence and severity of solicited adverse reactions that occurred within 7 days following one dose of Prevnar 13 administered to children 15 months through 59 months of age are shown in Tables 7 and 8.

Table 7: Percentage of Subjects 15 Months Through 59 Months of Age, Previously Vaccinated With 3 or 4 Prior Infant Doses of Prevnar, Reporting Solicited Local Reactions Within 7 Days After One Supplemental Prevnar 13 Vaccination [Study conducted in US NCT00761631 (Study 5).]
 | 15 months through 23 months [Dose 2 data not shown.] |  | 24 months through 59 months [The data for this age group are only represented as a single result as 95% of children received 4 doses of Prevnar prior to enrollment.]
Graded Local Reaction | 1 dose Prevnar 13 3 prior Prevnar doses N [Number of subjects reporting Yes for at least 1 day or No for all days.] =67–72 % | 1 dose Prevnar 13 4 prior Prevnar doses N=154–184 % | 1 dose Prevnar 13 3 or 4 prior Prevnar doses N=209–238 %
Redness [Diameters were measured in caliper units of whole numbers from 1 to 14 or 14+. One caliper unit = 0.5 cm. Measurements were rounded up to the nearest whole number. Intensity of redness and swelling were then characterized as Mild (0.5–2.0 cm), Moderate (2.5–7.0 cm), or Severe (>7.0 cm).]
Any | 26.4 | 28.2 | 35.4
Mild | 18.8 | 24.3 | 31.1
Moderate | 11.4 | 7.5 | 12.1
Severe | 1.5 | 0.0 | 0.0
Swelling
Any | 23.9 | 19.6 | 20.7
Mild | 18.6 | 16.4 | 17.2
Moderate | 8.8 | 8.1 | 7.5
Severe | 0.0 | 0.0 | 0.0
Tenderness
Any | 48.6 | 47.3 | 62.6
Interferes with limb movement | 5.9 | 6.4 | 10.7

Table 8: Percentage of Subjects 15 Months Through 59 Months of Age, Previously Vaccinated With 3 or 4 Prior Infant Prevnar Doses, Reporting Solicited Systemic Adverse Reactions Within 7 Days After One Supplemental Prevnar 13 Vaccination [Study conducted in US NCT00761631 (Study 5).]
 | 15 through 23 months [Dose 2 data not shown.] |  | 24 months through 59 months [The data for this age group are only represented as a single result as 95% of children received 4 doses of Prevnar prior to enrollment.]
Systemic Reaction | 1 dose Prevnar 13 3 prior Prevnar doses N [Number of subjects reporting Yes for at least 1 day or No for all days.] =66–75 % | 1 dose Prevnar 13 4 prior Prevnar doses N=154–189 % | 1 dose Prevnar 13 3 or 4 prior Prevnar doses N=209–236 %
Fever [Fever gradings: Mild (≥38°C but ≤39°C), Moderate (>39°C but ≤40°C), and Severe (>40°C). No other systemic event other than fever was graded.]
Any | 19.1 | 19.9 | 8.1
Mild | 16.2 | 17.4 | 7.6
Moderate | 6.1 | 3.9 | 1.9
Severe | 0.0 | 0.0 | 0.5
Decreased appetite | 44.4 | 39.3 | 28.1
Irritability | 73.3 | 65.1 | 45.8
Increased sleep | 35.2 | 35.3 | 18.8
Decreased sleep | 25.0 | 29.7 | 14.8

Clinical Trials Experience With Prevnar 13 in Children 5 Through 17 Years of Age

In a US study^5 (Study 5), the safety of Prevnar 13 was evaluated in children 5 through 9 years of age previously immunized with at least one dose of Prevnar, and in children 10 through 17 years of age with no prior pneumococcal vaccination. In this open label trial, 592 children, including those with asthma, received a single dose of Prevnar 13. The percentage of children 5 through 9 years of age who received 3 and 4 prior doses of Prevnar was 29.1% and 54.5% respectively.

Most subjects were White (72.8%), 21.8% were Black or African-American, and 1.5% were Asian; 91.4% of subjects were non-Hispanic and non-Latino and 8.6% were Hispanic or Latino. Overall, 51.2% of subjects were male.

The incidence and severity of solicited adverse reactions that occurred within 7 days following one dose of Prevnar 13 administered to children 5 through 17 years of age are shown in Tables 9 and 10.

Table 9: Percentage of Subjects 5 Through 17 Years of Age, Reporting Solicited Local Reactions Within 7 Days After Prevnar 13 Vaccination [Study conducted in US NCT00761631 (Study 5).]
 | Vaccine Group (as Administered)
 | Prevnar 13 (5 Through 9 Years) |  |  | Prevnar 13 (10 Through 17 Years)
Local Reaction | N [N = number of subjects reporting Yes for at least 1 day or No for all days.] | n [n = Number of subjects reporting the specific characteristic.] | % | N | n | %
Redness
Any | 233 | 100 | 42.9 | 232 | 70 | 30.2
Mild [Mild, 0.5 – 2.0 cm; moderate, 2.5 – 7.0 cm; severe, >7.0 cm.] | 226 | 63 | 27.9 | 226 | 48 | 21.2
Moderate | 218 | 48 | 22.0 | 221 | 31 | 14.0
Severe | 212 | 7 | 3.3 | 213 | 4 | 1.9
Swelling
Any | 226 | 85 | 37.6 | 233 | 86 | 36.9
Mild | 220 | 48 | 21.8 | 221 | 50 | 22.6
Moderate | 219 | 48 | 21.9 | 226 | 48 | 21.2
Severe | 211 | 7 | 3.3 | 214 | 4 | 1.9
Tenderness
Any | 265 | 230 | 86.8 | 283 | 252 | 89.0
Significant [Significant = present and interfered with limb movement.] | 221 | 43 | 19.5 | 242 | 106 | 43.8

Table 10: Percentage of Subjects 5 Through 17 Years of Age, Reporting Solicited Systemic Adverse Reactions Within 7 Days After Prevnar 13 Vaccination [Study conducted in US NCT00761631 (Study 5).]
 | Vaccine Group (as Administered)
 | Prevnar 13 (5 Through 9 Years) |  |  | Prevnar 13 (10 Through 17 Years)
Systemic Event | N [N = number of subjects reporting Yes for at least 1 day or No for all days.] | n [n = Number of subjects reporting the event.] | % | N | n | %
Any fever ≥38°C | 214 | 13 | 6.1 | 214 | 12 | 5.6
Mild [Fever gradings: Mild (≥38°C but ≤39°C), Moderate (>39°C but ≤40°C), and Severe (>40°C). No other systemic event other than fever was graded. Parents reported the use of antipyretic medication to treat or prevent symptoms in 45.1% and 33.1% of subjects 5 through 9 years of age and 10 through 17 years of age, respectively.] | 212 | 9 | 4.2 | 214 | 11 | 5.1
Moderate | 212 | 5 | 2.4 | 212 | 1 | 0.5
Severe | 210 | 1 | 0.5 | 212 | 1 | 0.5
Decreased appetite | 227 | 52 | 22.9 | 223 | 51 | 22.9
Irritability | 234 | 73 | 31.2 | 234 | 59 | 25.2
Increased sleep | 226 | 48 | 21.2 | 229 | 61 | 26.6
Decreased sleep | 212 | 12 | 5.7 | 224 | 42 | 18.8
Hives (urticaria) | 213 | 4 | 1.9 | 214 | 3 | 1.4

6.2 Clinical Trials Experience With Prevnar 13 in Adults ≥18 Years of Age

The safety of Prevnar 13 was assessed in 7 clinical studies (Studies 6–12) ^6–12 conducted in the US and Europe which included 91,593 adults (48,806 received Prevnar 13) ranging in age from 18 through 101 years.

The 48,806 Prevnar 13 recipients included 899 adults who were aged 18 through 49 years, 2,616 adults who were aged 50 through 64 years, 45,291 adults aged 65 years and older. Of the 48,806 Prevnar 13 recipients, 46,890 adults had not previously received Pneumovax® 23 (pneumococcal polysaccharide vaccine [23-valent], PPSV23) ("PPSV23 unvaccinated") and 1,916 adults were previously vaccinated ("PPSV23 previously vaccinated") with PPSV23 at least 3 years prior to enrollment.

Safety and Immunogenicity Studies

Safety and immunogenicity of Prevnar 13 is supported by 6 clinical studies. Study 6^6 evaluated the safety and immunogenicity of Prevnar 13 in adults 18 through 64 years of age who had not received a previous dose of pneumococcal vaccine. Adults 18 through 59 years of age received a single dose of Prevnar 13, and adults 60 through 64 years of age received a single dose of Prevnar 13 or PPSV23.

Study 7 was randomized and compared the safety and immunogenicity of Prevnar 13 with PPSV23 as a single dose in adults ≥70 years vaccinated with PPSV23 (≥5 years prior to enrollment).^7 Study 8 was randomized and evaluated the safety and immunogenicity of Prevnar 13 and PPSV23 in different sequential order in PPSV23 naive adults aged 60 through 64 years^8.

One clinical safety study^9 (Study 9) of Prevnar 13, conducted in PPSV23 previously vaccinated (≥3 years prior to enrollment) adults aged ≥68 years was a single arm study. Two studies, one in the US^10 (Study 10) in adults aged 50 through 59 years and the other in Europe^11 (Study 11) in adults aged ≥65 years, evaluated the concomitant administration of Prevnar 13 with inactivated influenza vaccine, trivalent (Fluarix®, A/H1N1, A/H3N2, and B, Fall 2007/Spring 2008: IIV3) in these two age groups in PPSV23 unvaccinated adults.

The total safety population in the 6 safety and immunogenicity studies was 7,097. In 5 of the 6 safety and immunogenicity studies, more females than males were enrolled (50.2% – 61.8%). Across the 6 studies the racial distribution included: >85% White; 0.2%–10.7% Black or African American; 0%–1.7% Asian; <1% Native Hawaiian or other Pacific Islander; ≤1%, American Indian or Alaskan Native. Ethnicity data were not collected in Study 11; in the 5 other studies 0.6%–4.8% were Hispanic or Latino.

In five studies,^6–8,10,11 subjects with pre-existing underlying diseases were enrolled if the medical condition was stable (did not require a change in therapy or hospitalization for worsening disease for 12 weeks before receipt of study vaccine) except in Study 9 where subjects were enrolled if the medical condition was stable for 6 or more weeks before receipt of study vaccine.

In the 6 safety and immunogenicity studies,^6–11 subjects were excluded from study participation due to prior receipt of diphtheria toxoid-containing vaccines within 6 months of study vaccine. However, the time of prior receipt of a diphtheria toxoid-containing vaccine was not recorded.

Solicited adverse reactions for Prevnar 13 in the safety and immunogenicity studies were monitored by subjects recording local adverse reactions and systemic reactions daily using an electronic diary for 14 consecutive days following vaccination. Unsolicited serious and non-serious adverse events were collected for one month after each vaccination. In addition, serious adverse events were collected for an additional 5 months after each vaccination (at the 6-month follow-up phone contact) in all studies except Study 11.

Following licensure of Prevnar 13 in adults ≥50 years of age, a randomized, double-blind, placebo-controlled US study (Study 13) was conducted to evaluate concomitant administration of Prevnar 13 with inactivated influenza vaccine, quadrivalent (Fluzone® Quadrivalent, A/H1N1, A/H3N2, B/Brisbane, and B/Massachusetts, Fall 2014/Spring 2015: IIV4) in PPSV23 previously vaccinated adults ≥50 years of age. Unsolicited serious and non-serious adverse events were collected as described above for Studies 6–10.

Efficacy Study

Study 12^12 was a randomized double-blind placebo-controlled study conducted in the Netherlands in community-dwelling adults aged 65 years and older with no prior pneumococcal vaccination history. A total of 84,496 subjects received either a single dose of Prevnar 13 (42,240) or placebo (42,256) in a 1:1 randomization. Among the 84,496 subjects, 58,072 (68.7%) were ≥65 to <75 years of age, 23,481 (27.8%) were ≥75 and <85 years of age, and 2,943 (3.5%) were ≥85 years of age. In the total safety population, more males (55.9%) were enrolled than females. The racial distribution was 98.5% White, 0.3% Black, 0.7% Asian, 0.5% Other, with <0.1% having missing data.

Adults with immunocompromising conditions or receiving immunosuppressive therapy and adults residing in a long-term care facility or requiring semiskilled nursing care were excluded. Adults with pre-existing medical conditions, as well as subjects with a history of smoking were eligible for enrollment. In the safety population, 42.3% of subjects had pre-existing medical conditions including heart disease (25.4%), lung disease or asthma (15.1%) and type 1 and type 2 diabetes mellitus (12.5%). Smoking was reported at baseline by 12.3% of the subjects.

For a subset of 2,011 subjects (1,006 Prevnar 13 recipients and 1,005 placebo recipients), solicited adverse reactions were monitored by recording local and systemic events using electronic diaries for 7 days after vaccination; unsolicited adverse events were collected for 28 days after vaccination, and serious adverse events were collected for 6 months after vaccination. For the remaining 41,231 Prevnar 13 and 41,250 placebo vaccinated subjects, serious adverse events were collected for 28 days after vaccination.

Serious Adverse Events in Adult Clinical Studies

Safety and Immunogenicity Studies

Across the 6 safety and immunogenicity studies,^6–11 serious adverse events within 1 month of vaccination were reported after an initial study dose in 0.2%–1.4% of 5,057 subjects vaccinated with Prevnar 13, and in 0.4%–1.7% of 1,124 subjects vaccinated after an initial study dose of PPSV23. From 1 month to 6 months after an initial study dose, serious adverse events were reported in 0.2%–5.8% of subjects vaccinated during the studies with Prevnar 13 and in 2.4%–5.5% of subjects vaccinated with PPSV23. One case of erythema multiforme occurred 34 days after receipt of a second dose of Prevnar 13.

Twelve of 5,667 (0.21%) Prevnar 13 recipients and 4 of 1,391 (0.29 %) PPSV23 recipients died. Deaths occurred between Day 3 and Day 309 after study vaccination with Prevnar 13 or PPSV23. Two of 12 deaths occurred within 30 days of vaccination and both deaths were in subjects >65 years of age. One death due to cardiac failure occurred 3 days after receiving placebo. This subject had received Prevnar 13 and IIV3 one month earlier. The other death was due to peritonitis 20 days after receiving Prevnar 13. The reported causes of the 10 remaining deaths occurring greater than 30 days after receiving Prevnar 13 were cardiac disorders (4), neoplasms (4), Mycobacterium avium complex pulmonary infection (1) and septic shock (1).

Efficacy Study

In Study 12^12 (subjects 65 years and older), serious adverse events within 1 month of vaccination were reported in 327 of 42,237 (0.8%) Prevnar 13 recipients (352 events) and in 314 of 42,225 (0.7%) placebo recipients (337 events). In the subset of subjects where serious adverse events were monitored for 6 months, 70 of 1,006 (7%) Prevnar 13 vaccinated subjects (90 events) and 60 of 1,005 (6%) placebo vaccinated subjects (69 events) reported serious adverse events.

During the follow-up period (average of 4 years) for case accumulation there were 3,006 deaths (7.1%) in the Prevnar 13 group and 3,005 deaths (7.1%) in the placebo group. There were 10 deaths (<0.1%) in the Prevnar 13 group and 10 deaths (<0.1%) in the placebo group within 28 days of vaccination. There were 161 deaths (0.4%) in the Prevnar 13 group and 144 deaths (0.3%) in the placebo group within 29 days – 6 months following vaccination. These data do not provide evidence for a causal relationship between deaths and vaccination with Prevnar 13.

Solicited Adverse Reactions in Adult Clinical Studies

The incidence and severity of solicited adverse reactions that occurred within 7 or 14 days following each dose of Prevnar 13, PPSV23, or placebo administered to adults in 5 studies are shown in Tables 11, 12, 13, and 14.

The commonly reported local adverse reactions after Prevnar 13 vaccination in PPSV23 unvaccinated and PPSV23 previously vaccinated adults were redness, swelling and pain at the injection site, or limitation of arm movement (Tables 11 and 12). The commonly reported systemic adverse reactions in PPSV23 unvaccinated and PPSV23 previously vaccinated adults were fatigue, headache, chills, rash, decreased appetite, or muscle pain and joint pain (Tables 13 and 14).

Table 11 - Percentage of Subjects With Solicited Local Adverse Reactions Within 7 or 14 Days in PPSV23 Unvaccinated Adults [Studies conducted in US NCT00427895 (Study 6) and NCT00574548 (Study 8) reported local reactions within 14 days. Study conducted in the Netherlands NCT00744263 (Study 12) reported local reactions within 7 days.]
 | Study 6 |  |  |  | Study 8 |  | Study 12
Age in Years | 18–49 | 50–59 | 60–64 |  | 60–64 |  | ≥65
Local Reaction | Prevnar 13 [Open label administration of Prevnar 13.] N [Number of subjects with known values (number of subjects reporting yes for at least one day or no for all days).] =266–787 % | Prevnar 13 N=152–322 % | Prevnar 13 N=193–331 % | PPSV23 N=190–301 % | Prevnar 13 N=270–370 % | PPSV23 N=134–175 % | Prevnar 13 N=886–914 % | Placebo N=859–865 %
Redness [Diameters were measured in caliper units of whole numbers from 1 to 21 or 21+. One caliper unit = 0.5 cm. Measurements were rounded up to the nearest whole number. Intensity of redness and swelling were then characterized as Mild = 2.5 to 5.0 cm, Moderate = 5.1 to 10.0 cm, and Severe is >10.0 cm.]
Any | 30.5 | 15.8 | 20.2 | 14.2 | 12.2 | 11.2 | 4.9 [Statistically significant difference p <0.05. No adjustments for multiplicity.] | 1.2
Mild | 26.4 | 15.2 | 15.9 | 11.2 | 8.3 | 9.7 | 3.7 | 0.8
Moderate | 11.9 | 5.0 | 8.6 | 4.9 | 6.4 | 3.9 | 1.7 | 0.3
Severe | 2.8 | 0.7 | 1.7 | 0.0 | 1.2 | 0.8 | 0.5 | 0.1
Swelling
Any | 39.4 | 21.7 | 19.3 | 13.1 | 10.0 | 10.4 | 6.8 | 1.2
Mild | 37.2 | 20.6 | 15.6 | 10.1 | 8.2 | 6.1 | 5.5 | 0.7
Moderate | 15.1 | 4.3 | 8.2 | 4.4 | 3.8 | 7.6 | 2.6 | 0.6
Severe | 1.4 | 0.0 | 0.6 | 1.1 | 0.0 | 0.0 | 0.1 | 0.1
Pain [Mild = awareness of symptom but easily tolerated, Moderate = discomfort enough to cause interference with usual activity, Severe = incapacitating with inability to do usual activity.]
Any | 96.7 | 88.8 | 80.1 | 73.4 | 69.2 | 58.3 | 36.1 | 6.1
Mild | 93.2 | 85.9 | 78.6 | 68.6 | 66.1 | 52.9 | 32.9 | 5.6
Moderate | 77.1 | 39.5 | 23.3 | 30.0 | 20.1 | 21.7 | 7.7 | 0.6
Severe | 16.0 | 3.6 | 1.7 | 8.6 | 2.3 | 0.8 | 0.3 | 0.1
Limitation of arm movement [Mild = some limitation of arm movement, Moderate = unable to move arm above head but able to move arm above shoulder, and Severe = unable to move arm above shoulder.]
Any | 75.2 | 40.7 | 28.5 | 30.8 | 23.5 | 28.2 | 14.1 | 3.2
Mild | 71.5 | 38.6 | 26.9 | 29.3 | 22.7 | 26.1 | 12.4 | 2.5
Moderate | 18.5 | 2.9 | 2.2 | 3.8 | 1.2 | 3.1 | 1.7 | 0.5
Severe | 15.6 | 2.9 | 1.7 | 4.3 | 1.1 | 2.3 | 1.2 | 0.7

Table 12 - Percentage of Subjects With Solicited Local Adverse Reactions in PPSV23 Previously Vaccinated Adults [Study conducted in US and Sweden NCT00546572 (Study 7) reported local reactions within 14 days. Study conducted in US, Sweden and Germany NCT00500266 (Study 9) reported local reactions within 14 days.]
 | Study 7 |  | Study 9
Age in Years | ≥70 |  | ≥68
Local Reaction | Prevnar 13 N [Number of subjects with known values.] =306–362 % | PPSV23 N=324–383 % | Prevnar 13 [Open label administration of Prevnar 13.] N=664–777 %
Redness [Diameters were measured in caliper units of whole numbers from 1 to 21 or 21+. One caliper unit = 0.5 cm. Measurements were rounded up to the nearest whole number. Intensity of redness and swelling were then characterized as Mild = 2.5 to 5.0 cm, Moderate = 5.1 to 10.0 cm, and Severe is >10.0 cm.]
Any | 10.8 | 22.2 [Statistically significant difference p <0.05. No adjustments for multiplicity.] | 14.3
Mild | 9.5 | 13.5 | 12.6
Moderate | 4.7 | 11.5 | 6.5
Severe | 1.7 | 4.8 | 1.1
Swelling
Any | 10.4 | 23.1 | 12.8
Mild | 8.9 | 14.0 | 10.9
Moderate | 4.0 | 13.6 | 5.5
Severe | 0.0 | 4.8 | 0.6
Pain [Mild = awareness of symptom but easily tolerated, Moderate = discomfort enough to cause interference with usual activity, Severe = incapacitating with inability to do usual activity.]
Any | 51.7 | 58.5 | 51.0
Mild | 50.1 | 54.1 | 49.4
Moderate | 7.5 | 23.6 | 9.0
Severe | 1.3 | 2.3 | 0.2
Limitation of arm movement [Mild = some limitation of arm movement, Moderate = unable to move arm above head but able to move arm above shoulder, and Severe = unable to move arm above shoulder.]
Any | 10.5 | 27.6 | 16.2
Mild | 10.3 | 25.2 | 14.8
Moderate | 0.3 | 2.6 | 1.6
Severe | 0.7 | 3.0 | 1.6

Table 13 - Percentage of Subjects With Solicited Systemic Events in PPSV23 Unvaccinated Adults [Studies conducted in US NCT00427895 (Study 6) and NCT00574548 (Study 8) reported systemic events within 14 days. Study conducted in the Netherlands NCT00744263 (Study 12) reported systemic events within 7 days.]
 | Study 6 |  |  |  | Study 8 |  | Study 12
Age in Years | 18–49 | 50–59 | 60–64 |  | 60–64 |  | ≥65
 | Prevnar 13 [Open label administration of Prevnar 13.] N [Number of subjects with known values (number of subjects reporting yes for at least one day or no for all days).] =221–561 % | Prevnar 13 N=137–248 % | Prevnar 13 N=174–277 % | PPSV23 N=176–273 % | Prevnar 13 N=261–328 % | PPSV23 N=127–173 % | Prevnar 13 N=881–896 % | Placebo N=860–878 %
Systemic Event
Fever
≥38.0°C | 7.2 | 1.5 | 4.0 | 1.1 | 4.2 | 1.6 | 2.9 [Statistically significant difference p <0.05. No adjustments for multiplicity.] | 1.3
38.0°C to 38.4°C | 4.2 | 1.5 | 4.0 | 1.1 | 3.8 | 0.8 | 1.1 | 0.6
38.5°C to 38.9°C | 1.9 | 0.0 | 0.6 | 0.0 | 0.8 | 0.0 | 0.6 | 0.2
39.0°C to 40.0°C | 1.4 | 0.0 | 0.0 | 0.0 | 0.4 | 0.8 | 0.7 | 0.2
>40.0°C [Fevers >40.0°C were confirmed to be data entry errors and remain in the table for the following: 1 case in the 18- to 49- year-old cohort (Study 6), and 7 cases in the Prevnar 13 group and 3 cases in placebo group (Study 12). For the other cohorts in Study 6 and for Study 8, data entry errors were removed.] | 0.5 | 0.0 | 0.0 | 0.0 | 0.0 | 0.0 | 0.8 | 0.3
Fatigue | 80.5 | 63.3 | 63.2 | 61.5 | 50.5 | 49.1 | 18.8 | 14.8
Headache | 81.4 | 65.9 | 54.0 | 54.4 | 49.7 | 46.1 | 15.9 | 14.8
Chills | 38.1 | 19.6 | 23.5 | 24.1 | 19.9 | 26.9 | 9.4 | 8.4
Rash | 21.3 | 14.2 | 16.5 | 13.0 | 8.6 | 13.4 | 3.3 | 0.8
Vomiting | 15.0 | 6.9 | 3.9 | 5.4 | 3.1 | 3.1 | 0.3 | 0.9
Decreased appetite | 55.6 | 25.3 | 21.3 | 21.7 | 14.7 | 23.0 | 5.3 | 3.7
Generalized new muscle pain | 82.0 | 61.8 | 56.2 | 57.8 | 46.9 | 51.5 | 18.4 | 8.4
Generalized aggravated muscle pain | 55.9 | 39.9 | 32.6 | 37.3 | 22.0 | 32.5 | 9.1 | 4.4
Generalized new joint pain | 41.7 | 31.5 | 24.4 | 30.1 | 15.5 | 23.8 | 7.4 | 5.4
Generalized aggravated joint pain | 28.6 | 25.6 | 24.9 | 21.4 | 14.0 | 21.1 | 5.2 | 4.2

Table 14 - Percentage of Subjects With Systemic Events in PPSV23 Previously Vaccinated Adults [Study conducted in US and Sweden NCT00546572 (Study 7) reported systemic events within 14 days. Study conducted in US, Sweden and Germany NCT00500266 (Study 9) reported systemic events within 14 days.]
 | Study 7 |  | Study 9
Age in Years | ≥70 |  | ≥68
 | Prevnar 13 N [Number of subjects with known values.] =299–350 % | PPSV23 N=303–367 % | Prevnar 13 [Open label administration of Prevnar 13.] N=635–733 %
Systemic Event
Fever
≥38.0°C | 1.0 | 2.3 | 1.1
38.0°C to 38.4°C | 1.0 | 2.0 | 0.8
38.5°C to 38.9°C | 0.0 | 0.0 | 0.0
39.0°C to 40.0°C | 0.0 | 0.3 | 0.3
>40.0°C | 0.0 | 0.0 | 0.0
Fatigue | 34.0 | 43.3 [Statistically significant difference p <0.05. No adjustments for multiplicity.] | 34.4
Headache | 23.7 | 26.0 | 26.1
Chills | 7.9 | 11.2 | 7.5
Rash | 7.3 | 16.4 | 8.4
Vomiting | 1.7 | 1.3 | 0.9
Decreased appetite | 10.4 | 11.5 | 11.2
Generalized new muscle pain | 36.8 | 44.7 | 25.3
Generalized aggravated muscle pain | 20.6 | 27.5 | 12.3
Generalized new joint pain | 12.6 | 14.9 | 12.8
Generalized aggravated joint pain | 11.6 | 16.5 | 9.7

Safety Results from Adult Clinical Study of Concomitant Administration of Prevnar 13 and IIV4 (Fluzone Quadrivalent) (Study 13)

The safety profile of Prevnar 13 when administered concomitantly with seasonal inactivated influenza vaccine, quadrivalent, to PPSV23 previously vaccinated adults ≥50 years of age was generally consistent with the known safety profile of Prevnar 13.

6.3 Post-marketing Experience With Prevnar 13 in Infants and Toddlers

The following adverse events have been reported through passive surveillance since market introduction of Prevnar 13. Because these events are reported voluntarily from a population of uncertain size, it is not always possible to reliably estimate their frequency or establish a causal relationship to the vaccine. The following adverse events were included based on one or more of the following factors: severity, frequency of reporting, or strength of evidence for a causal relationship to Prevnar 13 vaccine.

Administration site conditions: Vaccination-site dermatitis, vaccination-site pruritus, vaccination-site urticaria

Blood and lymphatic system disorders: Lymphadenopathy localized to the region of the injection site

Cardiac disorders: Cyanosis

Immune system disorders: Anaphylactic/anaphylactoid reaction including shock

Nervous system disorders: Hypotonia

Skin and subcutaneous tissue disorders: Angioneurotic edema, erythema multiforme

Respiratory: Apnea

Vascular disorders: Pallor

7 DRUG INTERACTIONS

7.1 Concomitant Immunizations

In clinical trials with infants and toddlers, Prevnar 13 was administered concomitantly with the following US-licensed vaccines: Pediarix [Diphtheria and Tetanus Toxoids and Acellular Pertussis Adsorbed, Hepatitis B (Recombinant) and Inactivated Poliovirus Vaccine Combined] (DTaP-HBV-IPV) and ActHIB [Haemophilus b Conjugate Vaccine (Tetanus Toxoid Conjugate)] (PRP-T) for the first three doses and with PedvaxHIB [Haemophilus b Conjugate Vaccine (Meningococcal Protein Conjugate)] (PRP-OMP), M-M-R II [Measles, Mumps, Rubella Virus Vaccine Live] (MMR) and Varivax [Varicella Virus Vaccine Live], or ProQuad [Measles, Mumps, Rubella and Varicella Virus Vaccine Live] (MMRV) and VAQTA [Hepatitis A vaccine, Inactivated] (HepA) for dose 4 [see Clinical Studies (14.2) and Adverse Reactions (6.1)].

In children and adolescents, data are insufficient to assess the concomitant administration of Prevnar 13 with Human Papillomavirus Vaccine (HPV), Meningococcal Conjugate Vaccine (MCV4) and Tetanus Toxoid, Reduced Diphtheria Toxoid and Acellular Pertussis Vaccine, Adsorbed (Tdap).

In adults, Prevnar 13 was administered concomitantly with US-licensed inactivated influenza vaccines, trivalent and quadrivalent (Studies 10, 11 and 13)[see Clinical Studies (14.4) and Adverse Reactions (6.2)]. There are no data on the concomitant administration of Prevnar 13 with diphtheria toxoid-containing vaccines and other vaccines licensed for use in adults 50 years of age and older.

When Prevnar 13 is administered at the same time as another injectable vaccine(s), the vaccines should always be administered with different syringes and given at different injection sites.

Do not mix Prevnar 13 with other vaccines/products in the same syringe.

7.2 Immunosuppressive Therapies

Individuals with impaired immune responsiveness due to the use of immunosuppressive therapy (including irradiation, corticosteroids, antimetabolites, alkylating agents, and cytotoxic agents) may not respond optimally to active immunization.

7.3 Antipyretics

A post-marketing clinical study conducted in Poland using a non-US vaccination schedule (2, 3, 4, and 12 months of age) evaluated the impact of prophylactic oral acetaminophen on antibody responses to Prevnar 13. The data show that 3 doses of acetaminophen (the first dose administered at the time of each vaccination and the subsequent doses at 6 to 8 hour intervals) reduced the antibody response to some serotypes following the third dose of Prevnar 13, compared with responses among infants who received antipyretics only as needed for treatment. Reduced antibody responses were not observed after the fourth dose of Prevnar 13 when acetaminophen was administered prophylactically.

7.4 Prior Vaccination with PPSV23

Prior receipt of PPSV23 within 1 year results in diminished immune responses to Prevnar 13 compared to PPSV23 naïve individuals [see Clinical Studies (14.3)].

8 USE IN SPECIFIC POPULATIONS

8.1 Pregnancy

Risk Summary

All pregnancies have a risk of birth defect, loss, or other adverse outcomes. In the US general population, the estimated background risk of major birth defects and miscarriage in clinically recognized pregnancies is 2% to 4% and 15% to 20%, respectively. Available data on Prevnar 13 administered to pregnant women are insufficient to inform vaccine-associated risks in pregnancy.

A developmental toxicity study has been performed in female rabbits administered Prevnar 13 prior to mating and during gestation. Each dose was approximately 20 times the human dose. This study revealed no evidence of harm to the fetus due to Prevnar 13 (see 8.1 Data).

Data

Animal

In a developmental toxicity study, female rabbits were administered Prevnar 13 by intramuscular injection twice prior to mating (17 days and 3 days prior to mating) and twice during gestation (gestation days 10 and 24), 0.5 mL/rabbit/occasion (each dose approximately 20 times the human dose). No adverse effects on pre-weaning development were observed. There were no vaccine-related fetal malformations or variations.

8.2 Lactation

Risk Summary

Data are not available to assess the effects of Prevnar 13 on the breastfed infant or on milk production/excretion. The developmental and health benefits of breastfeeding should be considered along with the mother's clinical need for Prevnar 13 and any potential adverse effects on the breastfed child from Prevnar 13 or from the underlying maternal condition. For preventive vaccines, the underlying maternal condition is susceptibility to disease prevented by the vaccine.

8.4 Pediatric Use

Safety and effectiveness of Prevnar 13 in children below the age of 6 weeks have not been established.

8.5 Geriatric Use

Of the total number of Prevnar 13 recipients aged 50 years and older in clinical studies (N=47,907), 94.5% (45,291 of 47,907) were 65 years and older and 30.3 % (14,498 of 47,907) were 75 years and older [see Clinical Studies (14.1) and (14.3)].

8.6 High Risk Populations

Individuals with the diseases or conditions listed below are at increased risk of pneumococcal disease. Immunogenicity and safety data in these populations are limited.

Infants Born Prematurely

Immune responses elicited by Prevnar 13 administered on a US schedule to preterm infants have not been studied. When preterm infants (<37 weeks gestational age, N=100) were administered 4 doses of Prevnar 13 on a non-US schedule, the serotype-specific IgG antibody responses after the third and fourth dose were lower compared to responses among term infants (≥37 weeks gestational age, N=100) for some serotypes; the effectiveness of Prevnar 13 in preterm infants cannot be established from this study.

Children with Sickle Cell Disease

In an open-label, single-arm, descriptive study, 2 doses of Prevnar 13 were administered 6 months apart to children ≥6 to <18 years of age with sickle cell disease who previously received PPSV23 at least 6 months prior to enrollment. Children with a prior history of pneumococcal conjugate vaccination were excluded. For all vaccine serotypes, anti-pneumococcal opsonophagocytic activity (OPA) geometric mean antibody titers (GMTs) were higher after the first dose compared to pre-vaccination (N=95–131); OPA GMTs following the first and second dose were comparable. The effectiveness of Prevnar 13 in this specific population has not been established.

Individuals with Hematopoietic Stem Cell Transplant

In an open-label, single-arm, descriptive study, 4 doses of Prevnar 13 were administered to subjects ≥2 years of age (range 2 to 71 years) who had received an allogeneic hematopoietic stem cell transplant 3 to 6 months prior to enrollment. All subjects had a history of stable engraftment (absolute neutrophil count>1000/µL, platelet count >50,000/µL), and did not have uncontrolled graft versus host disease. The first three doses of Prevnar 13 were administered one month apart, followed by a fourth dose of Prevnar 13 six months after the third dose. Sera were obtained approximately one month after each vaccination. Immune responses (IgG GMCs) after the first dose of Prevnar 13 were numerically higher for all serotypes compared with baseline. In addition, after each subsequent dose of Prevnar 13, IgG GMCs for all serotypes were numerically higher than responses after the previous dose. A post hoc analysis of the immune responses as measured by OPA antibody assay showed the pattern of functional antibody responses to be consistent with IgG responses for each serotype. The effectiveness of Prevnar 13 in this specific population has not been established.

Individuals with HIV Infection

In an open-label, single-arm, descriptive study, 3 doses of Prevnar 13 were administered 6 months apart to HIV-infected adults ≥18 years of age (median age 48 years), with CD4 counts ≥200 cells/µL and serum HIV RNA titer <50,000 copies/mL. All subjects had been vaccinated previously with PPSV23 at least 6 months prior to enrollment. For all vaccine serotypes anti-pneumococcal OPA GMTs were numerically higher after the first dose compared to pre-vaccination (N=227–253); OPA GMTs following the first, second and third dose were generally comparable. The effectiveness of Prevnar 13 in this specific population has not been established.

In an open-label, single-arm, descriptive study, 3 doses of Prevnar 13 were administered 1 month apart to HIV-infected subjects ≥6 years of age with CD4 counts ≥200 cells/µL, and serum HIV RNA titer <50,000 copies/mL. Subjects had not previously been vaccinated with a pneumococcal vaccine. For all vaccine serotypes anti-pneumococcal OPA GMTs were numerically higher after the first dose compared to pre-vaccination (N=197–257); OPA GMTs following the first, second and third dose were generally comparable. The effectiveness of Prevnar 13 in this specific population has not been established.

11 DESCRIPTION

Prevnar 13, Pneumococcal 13-valent Conjugate Vaccine (Diphtheria CRM197 Protein) is a sterile suspension of saccharides of the capsular antigens of Streptococcus pneumoniae serotypes 1, 3, 4, 5, 6A, 6B, 7F, 9V, 14, 18C, 19A, 19F, and 23F, individually linked to non-toxic diphtheria CRM197 protein. Each serotype is grown in soy peptone broth. The individual polysaccharides are purified through centrifugation, precipitation, ultrafiltration, and column chromatography. The polysaccharides are chemically activated to make saccharides, which are directly conjugated by reductive amination to the protein carrier CRM197, to form the glycoconjugate. CRM197 is a nontoxic variant of diphtheria toxin isolated from cultures of Corynebacterium diphtheriae strain C7 (β197) grown in a casamino acids and yeast extract-based medium or in a chemically-defined medium. CRM197 is purified through ultrafiltration, ammonium sulfate precipitation, and ion-exchange chromatography. The individual glycoconjugates are purified by ultrafiltration and column chromatography and analyzed for saccharide to protein ratios, molecular size, free saccharide, and free protein.

The individual glycoconjugates are compounded to formulate Prevnar 13. Potency of the formulated vaccine is determined by quantification of each of the saccharide antigens and by the saccharide to protein ratios in the individual glycoconjugates. Each 0.5 mL dose of the vaccine is formulated to contain approximately 2.2 µg of each of Streptococcus pneumoniae serotypes 1, 3, 4, 5, 6A, 7F, 9V, 14, 18C, 19A, 19F, 23F saccharides, 4.4 μg of 6B saccharides, 34 µg CRM197 carrier protein, 100 µg polysorbate 80, 295 µg succinate buffer and 125 µg aluminum as aluminum phosphate adjuvant.

The tip cap and rubber plunger of the prefilled syringe are not made with natural rubber latex.

12 CLINICAL PHARMACOLOGY

12.1 Mechanism of Action

Prevnar 13, comprised of pneumococcal polysaccharides conjugated to a carrier protein (CRM197), elicits a T-cell dependent immune response. Protein carrier-specific T-cells provide the signals needed for maturation of the B-cell response.

Nonclinical and clinical data support opsonophagocytic activity, as measured by opsonophagocytic activity (OPA) antibody assay, as a contributor to protection against pneumococcal disease. The OPA antibody assay provides an in vitro measurement of the ability of serum antibodies to eliminate pneumococci by promoting complement-mediated phagocytosis and is believed to reflect relevant in vivo mechanisms of protection against pneumococcal disease. OPA antibody titers are expressed as the reciprocal of the highest serum dilution that reduces survival of the pneumococci by at least 50%.

In infants that have received Prevnar 13, opsonophagocytic activity correlates well with serotype specific anti-capsular polysaccharide IgG levels as measured by ELISA. A serum anti-capsular polysaccharide antibody concentration of 0.35 µg/mL as measured by ELISA one month after the third dose as a single antibody reference concentration was used to estimate the effectiveness of Prevnar 13 against invasive pneumococcal disease (IPD) in infants and children. The assay used for this determination is a standardized ELISA involving pre-absorption of the test sera with pneumococcal C-polysaccharide and serotype 22F polysaccharide to reduce non-specific background reactivity. The single antibody reference value was based on pooled efficacy estimates from three placebo-controlled IPD efficacy trials with either Prevnar or the investigational 9-valent CRM197 conjugate pneumococcal polysaccharide vaccine. This reference concentration is only applicable on a population basis and cannot be used to predict protection against IPD on an individual basis. Functional antibodies elicited by the vaccine (as measured by a dribble opsonophagocytic activity [dOPA] antibody assay) were also evaluated in infants.

In adults, an antipolysaccharide binding antibody IgG level to predict protection against invasive pneumococcal disease or non-bacteremic pneumonia has not been defined. Noninferiority trials for Prevnar 13 were designed to show that functional OPA antibody responses (as measured by a microcolony OPA [mcOPA] antibody assay) for the Prevnar 13 serotypes are noninferior and for some serotypes superior to the common serotypes in the currently licensed pneumococcal polysaccharide vaccine (PPSV23). OPA antibody titers measured in the mcOPA antibody assay cannot be compared directly to titers measured in the dOPA antibody assay.

13 NONCLINICAL TOXICOLOGY

13.1 Carcinogenesis, Mutagenesis, Impairment of Fertility

Prevnar 13 has not been evaluated for the potential to cause carcinogenicity, genotoxicity, or impairment of male fertility. In a study in rabbits, no vaccine-related effects were found regarding reproductive performance including female fertility [see Use in Specific Populations (8.1)].

14 CLINICAL STUDIES

14.1 Efficacy Data

Prevnar Efficacy Data

Invasive Pneumococcal Disease (IPD)

Prevnar (Pneumococcal 7-valent Conjugate Vaccine [Diphtheria CRM'197 Protein]) was licensed in the US for infants and children in 2000, following a randomized, double-blind clinical trial in a multiethnic population at Northern California Kaiser Permanente (NCKP) from October 1995 through August 20, 1998, in which 37,816 infants were randomized to receive either Prevnar or a control vaccine (an investigational meningococcal group C conjugate vaccine [MnCC]) at 2, 4, 6, and 12–15 months of age. In this study, the efficacy of Prevnar against invasive disease due to S. pneumoniae in cases accrued during this period was 100% in both the per-protocol and intent-to-treat analyses (95% confidence interval [CI]: 75.4%, 100% and 81.7%, 100%, respectively). Data accumulated through an extended follow-up period to April 20, 1999, resulted in similar efficacy estimates of 97.4% in the per-protocol analysis and 93.9% in the intent-to-treat analysis (95% CI: 82.7%, 99.9% and 79.6%, 98.5%, respectively).

Acute Otitis Media (AOM)

The efficacy of Prevnar against otitis media was assessed in two clinical trials: a trial in Finnish infants at the National Public Health Institute and the efficacy trial in US infants at Northern California Kaiser Permanente (NCKP).

The Finnish Otitis Media (FinOM) trial was a randomized, double-blind trial in which 1,662 infants were equally randomized to receive either Prevnar or a control vaccine Recombivax HB (Hepatitis B vaccine (Recombinant) [Hep B]) at 2, 4, 6, and 12–15 months of age. In this study, conducted between December 1995 and March 1999, parents of study participants were asked to bring their children to the study clinics if the child had respiratory infections or symptoms suggesting acute otitis media (AOM). If AOM was diagnosed, tympanocentesis was performed, and the middle-ear fluid was cultured. If S. pneumoniae was isolated, serotyping was performed; the primary endpoint was efficacy against AOM episodes caused by vaccine serotypes in the per-protocol population. In the NCKP trial, the efficacy of Prevnar against otitis media was assessed from the beginning of the trial in October 1995 through April 1998. The otitis media analysis included 34,146 infants randomized to receive either Prevnar (N=17,070), or the control vaccine (N=17,076), at 2, 4, 6, and 12–15 months of age. In this trial, no routine tympanocentesis was performed, and no standard definition of otitis media was used by study physicians. The primary otitis media endpoint was efficacy against all otitis media episodes in the per-protocol population.

The vaccine efficacy against AOM episodes due to vaccine serotypes assessed in the Finnish trial, was 57% (95% CI: 44%, 67%) in the per-protocol population and 54% (95% CI: 41%, 64%) in the intent-to-treat population. The vaccine efficacy against AOM episodes due to vaccine-related serotypes (6A, 9N, 18B, 19A, 23A), also assessed in the Finnish trial, was 51% (95% CI: 27, 67) in the per-protocol population and 44% (95% CI: 20, 62) in the intent-to-treat population. There was a nonsignificant increase in AOM episodes caused by serotypes unrelated to the vaccine in the per-protocol population, compared to children who received the control vaccine, suggesting that children who received Prevnar appeared to be at increased risk of otitis media due to pneumococcal serotypes not represented in the vaccine. However, vaccination with Prevnar reduced pneumococcal otitis media episodes overall. In the NCKP trial, in which the endpoint was all otitis media episodes regardless of etiology, vaccine efficacy was 7% (95% CI: 4%, 10%) and 6% (95% CI: 4%, 9%), respectively, in the per-protocol and intent-to-treat analyses. Several other otitis media endpoints were also assessed in the two trials.

Recurrent AOM, defined as 3 episodes in 6 months or 4 episodes in 12 months, was reduced by 9% in both the per-protocol and intent-to-treat populations (95% CI: 3%, 15% in per-protocol and 95% CI: 4%, 14% in intent-to-treat) in the NCKP trial; a similar trend was observed in the Finnish trial. The NCKP trial also demonstrated a 20% reduction (95% CI: 2, 35) in the placement of tympanostomy tubes in the per-protocol population and a 21% reduction (95% CI: 4, 34) in the intent-to-treat population. Data from the NCKP trial accumulated through an extended follow-up period to April 20, 1999, in which a total of 37,866 children were included (18,925 in Prevnar group and 18,941 in MnCC control group), resulted in similar otitis media efficacy estimates for all endpoints.

Prevnar 13 Adult Efficacy Data

The efficacy of Prevnar 13 against vaccine-type (VT) pneumococcal community-acquired pneumonia (CAP) and IPD was assessed in a randomized, double-blind, placebo-controlled study conducted over ~ 4 years in the Netherlands^12 (Study 12). A total of 84,496 subjects 65 years and older received a single dose of either Prevnar 13 or placebo in a 1:1 randomization; 42,240 subjects were vaccinated with Prevnar 13 and 42,256 subjects were vaccinated with placebo.

The primary objective was to demonstrate the efficacy of Prevnar 13 in the prevention of a first episode of confirmed VT-CAP (defined as presence of ≥2 specified clinical criteria; chest X-ray consistent with CAP as determined by a central committee of radiologists; and positive VT-specific Urinary Antigen Detection assay (UAD) or isolation of VT S. pneumoniae from blood or other sterile site). The secondary objectives were to demonstrate the efficacy of Prevnar 13 in the prevention of a first episode of 1) confirmed nonbacteremic/noninvasive (NB/NI) VT-CAP (an episode of VT-CAP for which the blood culture result and any other sterile site culture results were negative for S. pneumoniae) and 2) VT-IPD (the presence of S. pneumoniae in a sterile site).

Surveillance for suspected pneumonia and IPD began immediately after vaccination and continued through identification of a prespecified number of cases. Subjects who had a CAP or IPD episode with symptom onset less than 14 days after vaccination were excluded from all analyses.

The median duration of follow-up per subject was 3.93 years. Prevnar 13 demonstrated statistically significant vaccine efficacy (VE) in preventing first episodes of VT pneumococcal CAP, nonbacteremic/noninvasive (NB/NI) VT pneumococcal CAP, and VT-IPD (Table 15).

Table 15 - Vaccine Efficacy for the Primary and Secondary Efficacy Endpoints – Per-Protocol Population
 |  | Vaccine Group
 |  | Prevnar 13 | Placebo
 |  | N=42240 | N=42256
Efficacy Endpoint | Total Number of Episodes | n | n | VE (%) | (95.2% CI)
Primary endpoint: First case of confirmed VT pneumococcal CAP | 139 | 49 | 90 | 45.6 | (21.8, 62.5)
Secondary endpoint: First episode of confirmed NB/NI VT pneumococcal CAP | 93 | 33 | 60 | 45 | (14.2, 65.3)
Secondary endpoint: First episode of VT-IPD | 35 | 7 | 28 | 75 | (41.1, 90.9)
Abbreviations: CAP = community-acquired pneumonia; CI = confidence interval; NB/NI = nonbacteremic/noninvasive; IPD = invasive pneumococcal disease; VE = vaccine efficacy; VT = vaccine-type.

14.2 Prevnar 13 Clinical Trials in Children 6 Weeks Through 17 Years of Age

Infants and Children 6 Weeks Through 17 Months of Age

Prevnar 13 effectiveness against invasive pneumococcal disease was inferred from comparative studies to a US-licensed 7-valent pneumococcal conjugate vaccine, Prevnar, in which Prevnar 13 elicited antipolysaccharide binding and functional OPA antibodies, as measured by ELISA and dOPA assays, respectively. These studies were designed to evaluate immunologic noninferiority of Prevnar 13 to Prevnar.

Clinical trials have been conducted in the US using a 2, 4, 6, and 12–15 month schedule.

The US noninferiority study^2 (Study 2) was a randomized, double-blind, active-controlled trial in which 2 month-old infants were randomly assigned to receive either Prevnar 13 or Prevnar in a 1:1 ratio. The two vaccine groups were well balanced with respect to race, ethnicity, and age and weight at enrollment. Most subjects were White (69.1%), 19.6% were Black or African-American, and 2.4% were Asian; 82.1% of subjects were non-Hispanic and non-Latino and 17.3% were Hispanic or Latino. Overall, 54.0% of subjects were male infants.

In Study 2, immune responses were compared in subjects receiving either Prevnar 13 or Prevnar using a set of noninferiority criteria. Co-primary endpoints included the percentage of subjects with serum pneumococcal anti-capsular polysaccharide IgG ≥0.35 µg/mL measured one month after the third dose and serum pneumococcal anti-capsular polysaccharide IgG geometric mean concentrations (GMCs) one month after the fourth dose. The assay used for this determination was a standardized ELISA involving pre-absorption of the test sera with pneumococcal C-polysaccharide and serotype 22F polysaccharide to reduce non-specific background reactivity. Responses to the 7 common serotypes in Prevnar 13 and Prevnar recipients were compared directly. Responses to the 6 additional serotypes in Prevnar 13 recipients were each compared to the lowest response observed among the Prevnar serotypes in Prevnar recipients.

Pneumococcal Immune Responses Following Three Doses

In Study 2, the noninferiority criterion for the proportion of subjects with pneumococcal anti-capsular polysaccharide IgG antibody concentrations ≥0.35 μg/mL one month after the third dose was met for 10 of the 13 serotypes. The exceptions were serotypes 6B, 9V, and 3. Although the response to serotypes 6B and 9V did not meet the pre-specified noninferiority criterion, the differences were marginal.

The percentage of infants achieving pneumococcal anti-capsular polysaccharide IgG antibody concentrations ≥0.35 μg/mL one month after the third dose is shown below (Table 16).

Table 16: Percentage of Subjects With Anti-capsular Antibody Concentration ≥0.35 µg/mL One Month After a Three Dose Series Administered at 2, 4 and 6 Months of Age, Study 2 [Studies conducted in US NCT00373958 (Study 2).] , [Evaluable Immunogenicity Population.] , [Noninferiority was met when the lower limit of the 95% CI for the difference between groups (Prevnar 13 minus Prevnar) was greater than -10%.] , [Antibody measured by a standardized ELISA involving pre-absorption of the test sera with pneumococcal C-polysaccharide and serotype 22F polysaccharide to reduce non-specific background reactivity.]
Serotype | Prevnar 13 N=249–252 (95% CI) | Prevnar N=250–252 (95% CI) | Difference in % responders (95% CI)
Prevnar Serotypes
4 | 94.4 (90.9, 96.9) | 98.0 (95.4, 99.4) | -3.6 (-7.3, -0.1)
6B | 87.3 (82.5, 91.1) | 92.8 (88.9, 95.7) | -5.5 (-10.9, -0.1)
9V | 90.5 (86.2, 93.8) | 98.4 (96.0, 99.6) | -7.9 (-12.4, -4.0)
14 | 97.6 (94.9, 99.1) | 97.2 (94.4, 98.9) | 0.4 (-2.7, 3.5)
18C | 96.8 (93.8, 98.6) | 98.4 (96.0, 99.6) | -1.6 (-4.7, 1.2)
19F | 98.0 (95.4, 99.4) | 97.6 (99.4, 99.1) | 0.4 (-2.4, 3.4)
23F | 90.5 (86.2, 93.8) | 94.0 (90.4, 96.6) | -3.6 (-8.5, 1.2)
Additional Serotypes [Comparison for the 6 additional serotypes was to the lowest responder of the 7 common serotypes in Prevnar recipients, which for this analysis was serotype 6B (92.8%; 95% CI: 88.9, 95.7).]
1 | 95.6 (92.3, 97.8) |  | 2.8 (-1.3, 7.2)
3 | 63.5 (57.1, 69.4) |  | -29.3 (-36.2, -22.4)
5 | 89.7 (85.2, 93.1) |  | -3.1 (-8.3, 1.9)
6A | 96.0 (92.8, 98.1) |  | 3.2 (-0.8, 7.6)
7F | 98.4 (96.0, 99.6) |  | 5.6 (1.9, 9.7)
19A | 98.4 (96.0, 99.6) |  | 5.6 (1.9, 9.7)

Functional dOPA antibody responses were elicited for all 13 serotypes, as shown in Table 17.

Table 17: Pneumococcal dOPA Antibody Geometric Mean Titers One Month After a Three Dose Series Administered at 2, 4 and 6 Months of Age, Study 2 [Studies conducted in US NCT00373958 (Study 2).] , [The dOPA (opsonophagocytic activity) antibody assay measures the ability of immune sera, in conjunction with complement, to mediate the uptake and killing of S. pneumoniae by phagocytic cells.] , [Evaluable Immunogenicity Population.]
Serotype | Prevnar 13 N=91–94 (95% CI) | Prevnar N=89–94 (95% CI)
Prevnar Serotypes
4 | 359 (276, 468) | 536 (421, 681)
6B | 1055 (817, 1361) | 1514 (1207, 1899)
9V | 4035 (2933, 5553) | 3259 (2288, 4641)
14 | 1240 (935, 1646) | 1481 (1133, 1934)
18C | 276 (210, 361) | 376 (292, 484)
19F | 54 (40, 74) | 45 (34, 60)
23F | 791 (605, 1034) | 924 (709, 1204)
Additional Serotypes
1 | 52 (39, 69) | 4 (4, 5)
3 | 121 (92, 158) | 7 (5, 9)
5 | 91 (67, 123) | 4 (4, 4)
6A | 980 (783, 1226) | 100 (66, 152)
7F | 9494 (7339, 12281) | 128 (80, 206)
19A | 152 (105, 220) | 7 (5, 9)

Pneumococcal Immune Responses Following Four Doses

In Study 2, post-dose 4 antibody concentrations were higher for all 13 serotypes than those achieved after the third dose. The noninferiority criterion for pneumococcal anti-capsular polysaccharide GMCs after 4 doses was met for 12 of the 13 pneumococcal serotypes. The noninferiority criterion was not met for the response to serotype 3 (Table 18).

Table 18: Pneumococcal IgG GMCs (µg/mL) One Month After a Four Dose Series Administered at 2, 4, 6 and 12–15 Months, Study 2 [Studies conducted in US NCT00373958 (Study 2).] , [Evaluable Immunogenicity Population.] , [Noninferiority was declared if the lower limit of the 2-sided 95% CI for Geometric Mean Ratio (Prevnar 13:Prevnar) was greater than 0.5.] , [Antibody measured by a standardized ELISA involving pre-absorption of the test sera with pneumococcal C-polysaccharide and serotype 22F polysaccharide to reduce non-specific background reactivity.]
Serotype | Prevnar 13 N=232–236 (95% CI) | Prevnar N=222–223 (95% CI) | GMC Ratio (95% CI)
Prevnar Serotypes
4 | 3.73 (3.28, 4.24) | 5.49 (4.91, 6.13) | 0.68 (0.57, 0.80)
6B | 11.53 (9.99, 13.30) | 15.63 (13.80, 17.69) | 0.74 (0.61, 0.89)
9V | 2.62 (2.34, 2.94) | 3.63 (3.25, 4.05) | 0.72 (0.62, 0.85)
14 | 9.11 (7.95, 10.45) | 12.72 (11.22, 14.41) | 0.72 (0.60, 0.86)
18C | 3.20 (2.82, 3.64) | 4.70 (4.18, 5.28) | 0.68 (0.57, 0.81)
19F | 6.60 (5.85, 7.44) | 5.60 (4.87, 6.43) | 1.18 (0.98, 1.41)
23F | 5.07 (4.41, 5.83) | 7.84 (6.91, 8.90) | 0.65 (0.54, 0.78)
Additional Serotypes [Comparison for the 6 additional serotypes was to the lowest responder of the 7 common serotypes in Prevnar recipients, which for this analysis was serotype 9V (3.63; 95% CI 3.25, 4.05).]
1 | 5.06 (4.43, 5.80) |  | 1.40 (1.17, 1.66)
3 | 0.94 (0.83, 1.05) |  | 0.26 (0.22, 0.30)
5 | 3.72 (3.31, 4.18) |  | 1.03 (0.87, 1.20)
6A | 8.20 (7.30, 9.20) |  | 2.26 (1.93, 2.65)
7F | 5.67 (5.01, 6.42) |  | 1.56 (1.32, 1.85)
19A | 8.55 (7.64, 9.56) |  | 2.36 (2.01, 2.76)

Following the fourth dose, the functional dOPA antibody response for each serotype was quantitatively greater than the response following the third dose (see Table 19).

Table 19: Pneumococcal dOPA Antibody Geometric Mean Titers One Month After the Fourth Dose-Evaluable Toddler Immunogenicity Population, Study 2 [Studies conducted in US NCT00373958 (Study 2).] , [The dOPA (opsonophagocytic activity) antibody assay measures the ability of immune sera, in conjunction with complement, to mediate the uptake and killing of S. pneumoniae by phagocytic cells.]
Serotype | Prevnar 13 N=88–92 (95% CI) | Prevnar N=92–96 (95% CI)
Prevnar Serotypes
4 | 1180 (847, 1643) | 1492 (1114, 1999)
6B | 3100 (2337, 4111) | 4066 (3243, 5098)
9V | 11856 (8810, 15955) | 18032 (14125, 23021)
14 | 2002 (1453, 2760) | 2366 (1871, 2992)
18C | 993 (754, 1308) | 1722 (1327, 2236)
19F | 200 (144, 276) | 167 (121, 230)
23F | 2723 (1961, 3782) | 4982 (3886, 6387)
Additional Serotypes
1 | 164 (114, 237) | 5 (4, 6)
3 | 380 (300, 482) | 12 (9, 16)
5 | 300 (229, 393) | 5 (4, 6)
6A | 2242 (1707, 2945) | 539 (375, 774)
7F | 11629 (9054, 14938) | 268 (164, 436)
19A | 1024 (774, 1355) | 29 (19, 44)

Previously Unvaccinated Older Infants and Children 7 Months Through 5 Years of Age

In an open-label descriptive study of Prevnar 13 in Poland^4 (Study 4), children 7 months through 11 months of age, 12 months through 23 months of age and 24 months through 5 years of age (prior to the 6th birthday) who were naïve to pneumococcal conjugate vaccine, were given 3, 2 or 1 dose of Prevnar 13 respectively, according to the age-appropriate schedules in Table 2. Serum IgG concentrations were measured one month after the final dose in each age group and the data are shown in Table 20.

Table 20: Pneumococcal Anti-capsular Polysaccharide IgG Antibody Geometric Mean Concentrations (μg/mL) One Month After the Final Prevnar 13 Catch-Up Dose in Pneumococcal Vaccine Naïve Children 7 Months Through 5 Years of Age by Age Group, Study 4 [Studies conducted in Poland NCT00452452 (Study 4).] , [Open label administration of Prevnar 13.]
Serotype | 3 doses Prevnar 13 7 through 11 months N=83–84 (95% CI) | 2 doses Prevnar 13 12 through 23 months N=104–110 (95% CI) | 1 dose Prevnar 13 24 months through 5 years N=135–152 (95% CI)
1 | 2.88 (2.44, 3.39) | 2.74 (2.37, 3.16) | 1.78 (1.52, 2.08)
3 | 1.94 (1.68, 2.24) | 1.86 (1.60, 2.15) | 1.42 (1.23, 1.64)
4 | 3.63 (3.11, 4.23) | 4.28 (3.78, 4.86) | 3.37 (2.95, 3.85)
5 | 2.85 (2.34, 3.46) | 2.16 (1.89, 2.47) | 2.33 (2.05, 2.64)
6A | 3.72 (3.12, 4.45) | 2.62 (2.25, 3.06) | 2.96 (2.52, 3.47)
6B | 4.77 (3.90, 5.84) | 3.38 (2.81, 4.06) | 3.41 (2.80, 4.16)
7F | 5.30 (4.54, 6.18) | 5.99 (5.40, 6.65) | 4.92 (4.26, 5.68)
9V | 2.56 (2.21, 2.96) | 3.08 (2.69, 3.53) | 2.67 (2.32, 3.07)
14 | 8.04 (6.95, 9.30) | 6.45 (5.48, 7.59) | 2.24 (1.71, 2.93)
18C | 2.77 (2.39, 3.23) | 3.71 (3.29, 4.19) | 2.56 (2.17, 3.03)
19A | 4.77 (4.28, 5.33) | 4.94 (4.31, 5.65) | 6.03 (5.22, 6.97)
19F | 2.88 (2.35, 3.54) | 3.07 (2.68, 3.51) | 2.53 (2.14, 2.99)
23F | 2.16 (1.82, 2.55) | 1.98 (1.64, 2.39) | 1.55 (1.31, 1.85)
Note – ClinicalTrials.gov NCT number is as follows: NCT00452452 (Poland).

Children 15 Months Through 59 Months of Age Previously Vaccinated with Prevnar

In an open-label descriptive study in the US^5 (Study 5), children 15 months through 59 months previously vaccinated with 3 or 4 doses of Prevnar, received 2 doses of Prevnar 13 (children >15 through 23 months of age) or 1 dose of Prevnar 13 (children 24 months through 59 months of age). The data following one dose of Prevnar 13 in children 24 months through 59 months of age are shown in Table 21.

Table 21: Pneumococcal Anti-capsular Polysaccharide IgG Antibody Geometric Mean Concentrations (μg/mL) One Month After One Prevnar 13 Catch-Up Dose in Children 24 Through 59 Months of Age With 3 or 4 Prior Doses of Prevnar, US Catch-Up Study 5 [Studies conducted in US NCT00761631 (Study 5).] , [Open label administration of Prevnar 13.]
Serotype | 1 dose Prevnar 13 24 months through 59 months N=173–175 (95% CI)
1 | 2.43 (2.15, 2.75)
3 | 1.38 (1.17, 1.61)
5 | 2.13 (1.89, 2.41)
6A | 12.96 (11.04, 15.21)
7F | 4.22 (3.74, 4.77)
19A | 14.18 (12.37, 16.25)

Children 5 Through 17 Years of Age

In a US study^5 (Study 5), a single dose of Prevnar 13 was administered to children 5 through 9 years of age, who were previously vaccinated with at least one dose of Prevnar, and to pneumococcal vaccine-naïve children 10 through 17 years of age.

In children 5 through 9 years of age, serotype-specific IgG concentrations measured 1 month after vaccination were noninferior (i.e., the lower limit of the 2-sided 95% CI for the geometric mean ratio [GMR] of >0.5) to the corresponding IgG concentrations in toddlers (Study 3) 1 month after a fourth pneumococcal vaccination (after the 4th dose of Prevnar for the 7 common serotypes and after the 4th dose of Prevnar 13 for the 6 additional serotypes) as shown in Tables 22 and 23 respectively.

Table 22: Pneumococcal IgG GMCs (µg/mL) One Month After Vaccination for 7 Common Serotypes, Prevnar 13 in Children 5 through 9 Years of Age in Study 5 Relative to Prevnar in Study 3 (Post-toddler) [Studies conducted in US NCT00761631 (Study 5) and NCT00444457 (Study 3).] , [Evaluable Immunogenicity Population.] , [Noninferiority was declared if the lower limit of the 2-sided 95% CI for geometric mean ratio was greater than 0.5.]
 | Vaccine Group (as Enrolled/Randomized)
 | Prevnar 13 5 Through 9 Years (Study 5) |  |  | Prevnar Post-Toddler Dose (Study 3)
Serotype | n [n = Number of subjects with a determinate antibody concentration for the specified serotype.] | GMC [Geometric mean concentrations (GMCs) were calculated using all subjects with available data for the specified blood draw. GMC after a 4-dose vaccination series with Prevnar (Study 3, post-toddler).] | (95% CI [Confidence intervals (CIs) are back transformations of a confidence interval based on the Student t distribution for the mean logarithm of the concentrations.]) | n | GMC | (95% CI) | GMC Ratio [Ratio of GMCs: Prevnar 13 (Study 5) to Prevnar (Study 3) reference.] | (95% CI [CIs for the ratio are back transformations of a confidence interval based on the Student t distribution for the mean difference of the logarithms of the measures [Prevnar 13 (Study 5) – Prevnar (Study 3)].])
Common
4 | 169 | 8.45 | (7.24, 9.87) | 173 | 2.79 | (2.45, 3.18) | 3.03 | (2.48, 3.71)
6B | 171 | 53.56 | (45.48, 63.07) | 173 | 9.47 | (8.26, 10.86) | 5.66 | (4.57, 6.99)
9V | 171 | 9.51 | (8.38, 10.78) | 172 | 1.97 | (1.77, 2.19) | 4.83 | (4.10, 5.70)
14 | 169 | 29.36 | (24.78, 34.78) | 173 | 8.19 | (7.31, 9.18) | 3.58 | (2.93, 4.39)
18C | 171 | 8.23 | (7.13, 9.51) | 173 | 2.33 | (2.05, 2.65) | 3.53 | (2.91, 4.29)
19F | 171 | 17.58 | (14.95, 20.67) | 173 | 3.31 | (2.87, 3.81) | 5.31 | (4.29, 6.58)
23F | 169 | 11.26 | (9.79, 12.95) | 173 | 4.49 | (3.86, 5.23) | 2.51 | (2.04, 3.08)

Table 23: Pneumococcal IgG GMCs (µg/mL) One Month After Vaccination for Additional 6 Serotypes, Prevnar 13 in Children 5 through 9 Years of Age in Study 5 Relative to Prevnar 13 in Study 3 (Post-toddler) [Studies conducted in US NCT00761631 (Study 5) and NCT00444457 (Study 3).] , [Evaluable Immunogenicity Population.] . [Noninferiority was declared if the lower limit of the 2-sided 95% CI for geometric mean ratio was greater than 0.5.]
 | Vaccine Group (as Enrolled/Randomized)
 | Prevnar 13 5 Through 9 Years (Study 5) |  |  | Prevnar 13 Post-Toddler Dose (Study 3)
Serotype | n [n = Number of subjects with a determinate antibody concentration for the specified serotype.] | GMC [Geometric mean concentrations (GMCs) were calculated using all subjects with available data for the specified blood draw. GMC after a 4-dose vaccination series with Prevnar 13 (Study 3, post-toddler).] | (95% CI [Confidence intervals (CIs) are back transformations of a confidence interval based on the Student t distribution for the mean logarithm of the concentrations.]) | n | GMC | (95% CI) | GMC Ratio [Ratio of GMCs: Prevnar 13 (Study 5) to Prevnar 13 (Study 3).] | (95% CI [CIs for the ratio are back transformations of a confidence interval based on the Student t distribution for the mean difference of the logarithms of the measures [Prevnar 13 (Study 5) – Prevnar 13 (Study 3)].])
Additional
1 | 171 | 3.57 | (3.05, 4.18) | 1068 | 2.90 | (2.75, 3.05) | 1.23 | (1.07, 1.42)
3 | 171 | 2.38 | (2.07, 2.74) | 1065 | 0.75 | (0.72, 0.79) | 3.17 | (2.78, 3.62)
5 | 171 | 5.52 | (4.82, 6.32) | 1068 | 2.85 | (2.72, 2.98) | 1.94 | (1.71, 2.20)
6A | 169 | 21.51 | (18.15, 25.51) | 1063 | 7.11 | (6.78, 7.46) | 3.03 | (2.64, 3.47)
7F | 170 | 6.24 | (5.49, 7.08) | 1067 | 4.39 | (4.18, 4.61) | 1.42 | (1.24, 1.62)
19A | 170 | 17.18 | (15.01, 19.67) | 1056 | 8.44 | (8.05, 8.86) | 2.03 | (1.78, 2.32)

In children 10 through 17 years of age OPA GMTs, as measured by the mcOPA assay, 1 month after vaccination were noninferior (i.e., the lower limit of the 2-sided 95% CI for the GMR of >0.5) to mcOPA GMTs in the 5 through 9 year old group for 12 of 13 serotypes (except for serotype 3), as shown in Table 24.

Table 24: Comparison of Pneumococcal mcOPA GMTs One Month After Vaccination, Prevnar 13, in Children 10 through 17 Years of Age Relative to Prevnar 13 in Children 5 through 9 Years of Age [Studies conducted in US NCT00761631 (Study 5).] , [Evaluable Immunogenicity Population.] , [Noninferiority was declared if the lower limit of the 2-sided 95% CI for geometric mean ratio was greater than 0.5.] , [Individual mcOPA antibody assay values below the assay LLOQ (lower limit of quantitation) were set at 0.50*LLOQ for the purpose of calculating the mcOPA antibody GMT.]
 | Vaccine Group (as Enrolled)
 | Prevnar 13 (10 through 17 Years) |  |  | Prevnar 13 (5 through 9 Years)
Serotype | n [n= Number of subjects with a determinate antibody titer for the specified serotype.] | GMT [Geometric mean titers (GMTs) were calculated using all subjects with available data for the specified blood draw.] | (95% CI [Confidence intervals (CIs) are back transformations of a confidence interval based on the Student t distribution for the mean logarithm of the titers.]) | n | GMT | (95% CI) | GMT Ratio [Ratio of GMTs: Prevnar 13(10 through 17 years of age) to Prevnar 13 (5 through 9 years of age).] | (95% CI [CIs for the ratio are back transformations of a confidence interval based on the Student t distribution for the mean difference of the logarithms of the measures [Prevnar 13(10 through 17 years of age) – Prevnar 13(5 through 9 years of age)] Study 5.])
Common
4 | 188 | 6912 | (6101, 7831) | 181 | 4629 | (4017, 5334) | 1.5 | (1.24, 1.80)
6B | 183 | 14224 | (12316, 16427) | 178 | 14996 | (13164, 17083) | 0.9 | (0.78, 1.15)
9V | 186 | 4485 | (4001, 5028) | 180 | 4733 | (4203, 5328) | 0.9 | (0.80, 1.12)
14 | 187 | 6894 | (6028, 7884) | 176 | 4759 | (4120, 5497) | 1.4 | (1.19, 1.76)
18C | 182 | 6263 | (5436, 7215) | 175 | 8815 | (7738, 10041) | 0.7 | (0.59, 0.86)
19F | 184 | 2280 | (1949, 2668) | 178 | 1591 | (1336, 1893) | 1.4 | (1.14, 1.81)
23F | 187 | 3808 | (3355, 4323) | 176 | 3245 | (2819, 3736) | 1.2 | (0.97, 1.42)
Additional
1 | 189 | 322 | (275, 378) | 179 | 191 | (165, 221) | 1.7 | (1.36, 2.10)
3 | 181 | 114 | (101, 130) | 178 | 203 | (182, 226) | 0.6 | (0.48, 0.67)
5 | 183 | 360 | (298, 436) | 178 | 498 | (437, 568) | 0.7 | (0.57, 0.91)
6A | 182 | 9928 | (8457, 11655) | 178 | 7514 | (6351, 8891) | 1.3 | (1.05, 1.67)
7F | 185 | 6584 | (5829, 7436) | 178 | 10334 | (9099, 11737) | 0.6 | (0.53, 0.76)
19A | 187 | 1276 | (1132, 1439) | 180 | 1180 | (1048, 1329) | 1.1 | (0.91, 1.28)

14.3 Prevnar 13 Immunogenicity Clinical Trials in Adults

Six Phase 3 or Phase 4 clinical trials^6–8,10,11,13 were conducted in the US and Europe evaluating the immunogenicity of Prevnar 13 in different adult age groups, in individuals who were either not previously vaccinated with PPSV23 (PPSV23 unvaccinated) or who had received one dose of PPSV23 (PPSV23 previously vaccinated).

Each study included healthy adults and immunocompetent adults with stable underlying conditions including chronic cardiovascular disease, chronic pulmonary disease, renal disorders, diabetes mellitus, chronic liver disease, and medical risk conditions and behaviors (e.g., alcoholism and smoking) that are known to increase the risk of serious pneumococcal pneumonia and invasive pneumococcal disease. A stable medical condition was defined as a medical condition not requiring significant change in therapy (i.e., change to new therapy category due to worsening disease) or hospitalization for worsening disease 6–12 weeks prior to receipt of the study vaccine.

Immune responses elicited by Prevnar 13 and PPSV23 were measured by a mcOPA antibody assay for the 13 pneumococcal serotypes contained in Prevnar 13. Serotype-specific mcOPA antibody GMTs measured 1 month after each vaccination were calculated. For the 12 serotypes in common to both vaccines, noninferiority between vaccines was met if the lower limit of the 2-sided 95% confidence interval (CI) of the GMT ratio (Prevnar 13/PPSV23) was greater than 0.5.

The response to the additional serotype 6A, which is contained in Prevnar 13 but not in PPSV23, was assessed by demonstration of a ≥4-fold increase in the anti-6A mcOPA antibody titer above preimmunization levels. A statistically significantly greater response for Prevnar 13 was defined, for the difference in percentages (Prevnar 13 minus PPSV23) of adults achieving a ≥4-fold increase in anti-6A mcOPA antibody titer, as the lower limit of the 2-sided 95% CI greater than zero. For comparison of mcOPA antibody GMTs, a statistically greater response for serotype 6A was defined as the lower limit of the 2-sided 95% CI of the GMT ratio (Prevnar 13/PPSV23) greater than 2.

Of the 6 Phase 3 or Phase 4 clinical trials, 2 noninferiority trials^6,7 were conducted in which the immune responses to Prevnar 13 were compared with the immune responses to PPSV23; one in PPSV23 unvaccinated adults aged 18 through 64 years^6 (Study 6), and one in PPSV23 previously vaccinated adults aged ≥70 years^7 (Study 7). A third study compared immune responses to a single dose of Prevnar 13 to the response to Prevnar 13 administered one year after a dose of PPSV23 in adults aged 60 through 64 years who were PPSV23 unvaccinated at enrollment^8 (Study 8). The study also compared immune responses of PPSV23 as a single dose to the responses to PPSV23 administered one year after a dose of Prevnar 13. Two studies assessed the concomitant administration of Prevnar 13 with seasonal inactivated Fluarix (IIV3) in the US^10 (Study 10) and Europe^11 (Study 11). One study (Study 13) assessed the concomitant administration of Prevnar 13 with seasonal inactivated Fluzone Quadrivalent (IIV4) in PPSV23 previously vaccinated adults ≥50 years of age in the US.

Overall across the clinical studies evaluating the immunogenicity of Prevnar 13 in adults, persons 18 through 64 years of age responded at least as well as persons 65 years and older, the age group evaluated in a clinical endpoint efficacy trial.

Clinical Trials Conducted in PPSV23 Unvaccinated Adults

In an active-controlled modified [Modified double-blind means that the site staff dispensing and administering the vaccine were unblinded, but all other study personnel including the principal investigator and subject were blinded.] double-blind clinical trial^6 (Study 6) of Prevnar 13 in the US, PPSV23 unvaccinated adults aged 60 through 64 years were randomly assigned (1:1) to receive Prevnar 13 or PPSV23. In addition, adults aged 18 through 49 years and 50 through 59 years were enrolled and received one dose of Prevnar 13 (open-label).

In adults aged 60 through 64 years, the mcOPA antibody GMTs elicited by Prevnar 13 were noninferior to those elicited by PPSV23 for the 12 serotypes in common to both vaccines (see Table 24). In addition, the lower limit of the 95% confidence interval for the mcOPA antibody GMT ratio (Prevnar 13/PPSV23) was greater than 1 for 8 of the serotypes in common.

For serotype 6A, which is unique to Prevnar 13, the proportion of subjects with a ≥4-fold increase after Prevnar 13 (88.5%) was statistically significantly greater than after PPSV23 (49.3%) in PPSV23-unvaccinated adults aged 60 through 64 years. OPA antibody GMTs for serotype 6A were statistically significantly greater after Prevnar 13 compared with after PPSV23 (see Table 25).

The mcOPA antibody GMTs elicited by Prevnar 13 in adults aged 50 through 59 years were noninferior to the corresponding mcOPA antibody GMTs elicited by Prevnar 13 in adults aged 60 through 64 years for all 13 serotypes (see Table 25).

In adults aged 18 through 49 years, the mcOPA antibody GMTs elicited by Prevnar 13 were noninferior to those elicited by Prevnar 13 in adults aged 60 through 64 years for all 13 serotypes (see Table 25).

Table 25: mcOPA Antibody GMTs in PPSV23-Unvaccinated Adults Aged 18 Through 49 Years or Aged 50 Through 59 Years Given Prevnar 13 and in Adults Aged 60 Through 64 Years Given Prevnar 13 or PPSV23 (Study 6) [Study conducted in US NCT00427895 (Study 6).] , [Noninferiority was defined for the 13 serotypes in adults aged 18 to 49 years, for the 12 common serotypes in adults aged 60 to 64 years and for the 13 serotypes in adults aged 50 to 59 years as the lower limit of the 2-sided 95% CI for GMT ratio greater than 0.5.] , [mcOPA antibody for the 11 serotypes unique to PPSV23 but not contained in Prevnar 13 were not measured.] , [Individual mcOPA antibody assay values below the assay LLOQ (lower limit of quantitation) were set at 0.50*LLOQ for the purpose of calculating the mcOPA antibody GMT.] , [Evaluable Immunogenicity Population.]
 | Prevnar 13 | Prevnar 13 | Prevnar 13 | PPSV23 | Prevnar 13 18–49 Relative to 60–64 Years | Prevnar 13 50–59 Relative to 60–64 Years | Prevnar 13 Relative to PPSV23, 60–64 Years [For serotype 6A, which is unique to Prevnar 13, a statistically significantly greater response was defined for analysis in cohort 1 as the lower limit of the 2-sided 95% CI for the GMT ratio (Prevnar 13/PPSV23) greater than 2.]
Serotype | 18–49 Years [Open label administration of Prevnar 13.] N=836–866 | 50–59 Years N=350–384 | 60–64 Years N=359–404 | 60–64 Years N=367–402 | Prevnar 13 18–49 Relative to 60–64 Years | Prevnar 13 50–59 Relative to 60–64 Years | Prevnar 13 Relative to PPSV23, 60–64 Years [For serotype 6A, which is unique to Prevnar 13, a statistically significantly greater response was defined for analysis in cohort 1 as the lower limit of the 2-sided 95% CI for the GMT ratio (Prevnar 13/PPSV23) greater than 2.]
Serotype | GMT | GMT | GMT | GMT | GMT Ratio (95% CI) | GMT Ratio (95% CI) | GMT Ratio (95% CI)
1 | 353 | 211 | 158 | 119 | 2.4 (2.03, 2.87) | 1.3 (1.07, 1.65) | 1.3 (1.07, 1.65)
3 | 91 | 94 | 96 | 90 | 1.0 (0.84, 1.13) | 1.0 (0.82, 1.18) | 1.1 (0.89, 1.29)
4 | 4747 | 2904 | 2164 | 1405 | 2.3 (1.92, 2.76) | 1.3 (1.06, 1.70) | 1.5 (1.18, 2.00)
5 | 386 | 322 | 236 | 198 | 1.9 (1.55, 2.42) | 1.4 (1.08, 1.74) | 1.2 (0.95, 1.50)
6A [6A is a serotype unique to Prevnar 13 but not contained in PPSV23.] | 5746 | 4469 | 2766 | 343 | 2.2 (1.84, 2.67) | 1.6 (1.28, 2.03) | 8.1 (6.11, 10.67)
6B | 9813 | 3350 | 2212 | 998 | 4.9 (4.13, 5.93) | 1.5 (1.20, 1.91) | 2.2 (1.70, 2.89)
7F | 3249 | 1807 | 1535 | 829 | 2.9 (2.41, 3.49) | 1.2 (0.98, 1.41) | 1.9 (1.52, 2.26)
9V | 3339 | 2190 | 1701 | 1012 | 2.9 (2.34, 3.52) | 1.3 (1.08, 1.53) | 1.7 (1.40, 2.02)
14 | 2983 | 1078 | 733 | 819 | 4.9 (4.01, 5.93) | 1.5 (1.14, 1.89) | 0.9 (0.69, 1.16)
18C | 3989 | 2077 | 1834 | 1074 | 2.3 (1.91, 2.79) | 1.1 (0.89, 1.44) | 1.7 (1.32, 2.21)
19A | 1580 | 968 | 691 | 368 | 2.3 (2.02, 2.66) | 1.4 (1.17, 1.68) | 1.9 (1.53, 2.30)
19F | 1533 | 697 | 622 | 636 | 3.0 (2.44, 3.60) | 1.1 (0.89, 1.41) | 1.0 (0.78, 1.23)
23F | 1570 | 531 | 404 | 87 | 4.2 (3.31, 5.31) | 1.3 (0.96, 1.80) | 4.6 (3.37, 6.38)
GMT, Geometric Mean Titer.

Clinical Trials Conducted in PPSV23 Previously Vaccinated Adults

In a Phase 3 active-controlled, modified double-blind clinical trial^7 (Study 7) of Prevnar 13 in the US and Sweden, PPSV23 previously vaccinated adults aged ≥70 years who had received one dose of PPSV23 ≥5 years prior were randomly assigned (1:1) to receive either Prevnar 13 or PPSV23.

The mcOPA antibody GMTs elicited by Prevnar 13 were noninferior to those elicited by PPSV23 for the 12 serotypes in common, when Prevnar 13 or PPSV23 were administered at a minimum of 5 years after a prior dose of PPSV23. In addition, the lower limit of the 95% confidence interval for the mcOPA antibody GMT ratio (Prevnar 13/PPSV23) was greater than 1 for 9 of the serotypes in common.

For serotype 6A, which is unique to Prevnar 13, the proportion of subjects with a ≥4-fold increase in mcOPA antibody titers after Prevnar 13 (71.1%) was statistically significantly greater than after PPSV23 (27.3%) in PPSV23 previously vaccinated adults aged ≥70 years. mcOPA antibody GMTs for serotype 6A were statistically significantly greater after Prevnar 13 compared with after PPSV23.

This clinical trial demonstrated that in adults aged ≥70 years and previously vaccinated with PPSV23 ≥5 years prior, vaccination with Prevnar 13 elicited noninferior immune responses as compared with re-vaccination with PPSV23 (see Table 26).

Table 26: mcOPA Antibody GMTs in PPSV23-Previously Vaccinated Adults Aged ≥70 Years Given Prevnar 13 or PPSV23 (Study 7) [Study conducted in US and Sweden NCT00546572 (Study 7).] , [For the 12 common serotypes, noninferiority was defined as the lower limit of the 2-sided 95% CI for GMT ratio (Prevnar 13/PPSV23) greater than 0.5.] , [For serotype 6A, which is unique to Prevnar 13, a statistically significantly greater response was defined as the lower limit of the 2-sided 95% CI for the GMT ratio (Prevnar 13/PPSV23) greater than 2.] , [mcOPA antibody for the 11 serotypes unique to PPSV23 but not contained in Prevnar 13 were not measured.] , [Individual mcOPA antibody assay values below the assay LLOQ (lower limit of quantitation) were set at 0.50*LLOQ for the purpose of calculating the mcOPA antibody GMT.] , [Evaluable Immunogenicity Population.]
Serotype | Prevnar 13 N=400–426 | PPSV23 N=395–445 | Prevnar 13 Relative to PPSV23
Serotype | GMT | GMT | GMT Ratio | (95% CI)
1 | 93 | 66 | 1.4 | (1.14, 1.72)
3 | 59 | 53 | 1.1 | (0.92, 1.31)
4 | 613 | 263 | 2.3 | (1.76, 3.10)
5 | 100 | 61 | 1.6 | (1.35, 2.00)
6A [6A is a serotype unique to Prevnar 13 but not contained in PPSV23.] | 1056 | 160 | 6.6 | (5.14, 8.49)
6B | 1450 | 565 | 2.6 | (2.00, 3.29)
7F | 559 | 481 | 1.2 | (0.97, 1.39)
9V | 622 | 491 | 1.3 | (1.08, 1.49)
14 | 355 | 366 | 1.0 | (0.76, 1.23)
18C | 972 | 573 | 1.7 | (1.33, 2.16)
19A | 366 | 216 | 1.7 | (1.40, 2.07)
19F | 422 | 295 | 1.4 | (1.16, 1.77)
23F | 177 | 53 | 3.3 | (2.49, 4.47)
GMT, Geometric Mean Titer.

Clinical Trial of Sequential Vaccination of Prevnar 13 and PPSV23 in PPSV23 Unvaccinated Adults

In a randomized clinical trial conducted in PPSV23-unvaccinated adults 60 through 64 years of age^8 (Study 8), 223 subjects received PPSV23 followed by Prevnar 13 one year later (PPSV23/Prevnar 13), and 478 received only Prevnar 13. mcOPA antibody titers were measured 1 month after vaccination with Prevnar 13 and are shown in Table 26. mcOPA antibody GMTs in those that received Prevnar 13 one year after PPSV23 were diminished when compared to those who received Prevnar 13 alone. Similarly, in exploratory analyses in PPSV23 previously vaccinated adults ≥70 years of age in Study 7, diminished mcOPA antibody GMTs were observed in those that received Prevnar 13 one year after PPSV23 when compared to those who received Prevnar 13 alone.

Table 27: mcOPA Antibody GMTs for the Prevnar 13 Serotypes in PPSV23 Unvaccinated Adults Aged 60 Through 64 Years Given Prevnar 13 Alone or Prevnar 13 One Year After PPSV23 (Study 8) (PPSV23/Prevnar 13) [Study conducted in US NCT00574548 (Study 8).] , [Evaluable Immunogenicity Population.] , [mcOPA antibody for the 11 serotypes unique to PPSV23 but not contained in Prevnar 13 were not measured.] , [Individual mcOPA antibody assay values below the assay LLOQ (lower limit of quantitation) were set at 0.50*LLOQ for the purpose of calculating the mcOPA antibody GMT.]
 | Prevnar 13 N=410–457 |  | PPSV23/Prevnar 13 N=180–196
Serotype | GMT | (95% CI) | GMT | (95% CI)
1 | 219 | (191, 252) | 88 | (72, 109)
3 | 78 | (69, 88) | 54 | (45, 65)
4 | 2590 | (2257, 2973) | 988 | (802, 1218)
5 | 258 | (218, 305) | 112 | (90, 139)
6A [6A is a serotype unique to Prevnar 13 but not contained in PPSV23.] | 2947 | (2536, 3426) | 1210 | (962, 1522)
6B | 2165 | (1845, 2540) | 832 | (654, 1059)
7F | 1518 | (1339, 1721) | 407 | (342, 485)
9V | 1279 | (1142, 1432) | 495 | (426, 575)
14 | 790 | (663, 941) | 515 | (402, 659)
18C | 1683 | (1437, 1971) | 650 | (504, 839)
19A | 717 | (629, 818) | 299 | (248, 361)
19F | 812 | (702, 939) | 360 | (293, 442)
23F | 384 | (312, 472) | 142 | (104, 193)
GMT =Geometric Mean Titer.

Also in Study 8, 266 subjects received Prevnar 13 followed by PPSV23 one year later (Prevnar 13/PPSV23). mcOPA antibody GMTs following PPSV23 administered one year after Prevnar 13 (Prevnar 13/PPSV23) were noninferior to those following a single dose of PPSV23 (N=237) for the 12 common serotypes [the lower limit of the 95% CI for the GMT ratio [Prevnar 13/PPSV23 relative to PPSV23] was >0.5] (see Table 27). In Study 6, which was conducted in PPSV23-unvaccinated adults 60 through 64 years of age, 108 subjects received PPSV23 3.5 to 4 years after Prevnar 13 (Prevnar 13/PPSV23) and 414 received a single dose of PPSV23. Higher serotype-specific mcOPA antibody GMT ratios [(Prevnar 13/PPSV23) / PPSV23] were generally observed compared to the one year dosing interval in Study 8.

Table 28: mcOPA Antibody GMTs for the Prevnar 13 Serotypes in PPSV23-Unvaccinated Adults Aged 60 Through 64 Years Given PPSV23 One Year After Prevnar 13 Relative to PPSV23 Alone (Study 8) [Study conducted in US NCT00574548 (Study 8).] , [Evaluable Immunogenicity Population.] , [mcOPA antibody for the 11 serotypes unique to PPSV23 but not contained in Prevnar 13 were not measured.] , [Individual mcOPA antibody assay values below the assay LLOQ (lower limit of quantitation) were set at 0.50*LLOQ for the purpose of calculating the mcOPA antibody GMT.]
 | Prevnar 13/PPSV23 N=216–233 |  | PPSV23 N=214–229 |  | GMT Ratio (Prevnar 13/PPSV23) / PPSV23
Serotype | GMT | 95% CI | GMT | 95% CI | Ratio | 95% CI
1 | 155 | (131, 182) | 161 | (131, 198) | 1.0 | (0.74, 1.25)
3 | 127 | (111, 145) | 83 | (71, 98) | 1.5 | (1.23, 1.87)
4 | 1409 | (1202, 1651) | 1468 | (1139, 1893) | 1.0 | (0.71, 1.29)
5 | 220 | (184, 264) | 178 | (144, 222) | 1.2 | (0.93, 1.64)
6A [6A is a serotype unique to Prevnar 13 but not contained in PPSV23. Anti-6A mcOPA antibody GMTs were descriptive in nature.] | 1366 | (1122, 1663) | 400 | (306, 524) | 3.4 | (2.45, 4.77)
6B | 1345 | (1113, 1625) | 875 | (689, 1111) | 1.5 | (1.14, 2.08)
7F | 748 | (653, 857) | 719 | (598, 865) | 1.0 | (0.83, 1.31)
9V | 848 | (731, 984) | 824 | (694, 977) | 1.0 | (0.82, 1.29)
14 | 711 | (580, 872) | 869 | (677, 1115) | 0.8 | (0.59, 1.13)
18C | 1115 | (925, 1344) | 912 | (707, 1177) | 1.2 | (0.89, 1.67)
19A | 471 | (408, 543) | 390 | (318, 477) | 1.2 | (0.94, 1.55)
19F | 819 | (697, 963) | 626 | (504, 779) | 1.3 | (1.00, 1.71)
23F | 216 | (169, 277) | 84 | (62, 114) | 2.6 | (1.74, 3.79)
GMT =Geometric Mean Titer.

14.4 Concomitant Vaccine Administration

Infants and Toddlers

The concomitant administration of routine US infant vaccines [see Drug Interactions (7.1)] with Prevnar 13 was evaluated in two studies: Study 2 [see Clinical Studies (14.2)], Pneumococcal Immune Responses Following Three Doses^2, and the US lot consistency study^3 (Study 3). In Study 3, subjects were randomly assigned to receive one of 3 lots of Prevnar 13 or Prevnar in a 2:2:2:1 ratio. The total number of infants vaccinated was 663^2 (Study 2) and 1699^3 (Study 3). Immune responses to concomitant vaccine antigens were compared in infants receiving Prevnar and Prevnar 13. Responses to diphtheria toxoid, tetanus toxoid, pertussis, polio types 1, 2, and 3, hepatitis B, PRP-T, PRP-OMP, measles, and varicella antigens in Prevnar 13 recipients were similar to those in Prevnar recipients. Based on limited data, responses to mumps and rubella antigens in Prevnar 13 recipients were similar to those in Prevnar recipients.

Adults ≥50 Years of Age

Concomitant Administration with QIV

Prevnar 13 was administered to PPSV23 previously vaccinated adults ≥50 years of age concomitantly with a US-licensed inactivated influenza vaccine, quadrivalent (IIV4) (Fluzone Quadrivalent) for the 2014/2015 influenza season (Study 13) [see Adverse Reactions (6.2) and Drug Interactions (7.1)]. One study group received Prevnar 13 and IIV4 concurrently, followed approximately one month later by placebo. A second study group received IIV4 and placebo concurrently, followed approximately one month later by Prevnar 13.

Serotype-specific pneumococcal antibody responses were measured one month after Prevnar 13 vaccination as OPA GMTs. Noninferiority was demonstrated for each pneumococcal serotype if the lower limit of the 2-sided 95% CI for the GMT ratio (Prevnar 13 + IIV4 relative to Prevnar 13 alone) was >0.5. Although OPA antibody responses to Prevnar 13 generally appeared to be slightly lower when Prevnar 13 was administered concomitantly with IIV4 compared to Prevnar 13 administered alone, noninferiority was demonstrated for all Prevnar 13 pneumococcal serotypes evaluated in Study 13.

Strain-specific influenza antibody responses were measured one month after IIV4 as hemagglutinin inhibition assay (HAI) titers. HAI GMTs were evaluated for each IIV4 strain in Study 13. Noninferiority was demonstrated if the lower limit of the 2-sided 95% CI for the HAI GMT ratio (Prevnar 13 + IIV4 relative to IIV4 + Placebo) was >0.5. Noninferiority was demonstrated for each IIV4 vaccine strain evaluated in Study 13.

Concomitant Administration with TIV

Two randomized, double-blind clinical trials evaluated the immunogenicity of Prevnar 13 given with IIV3 (Fall 2007/ Spring 2008 Fluarix, A/H1N1, A/H3N2, and B strains) in PPSV23 unvaccinated adults aged 50 through 59 years^10 (Study 10, conducted in the US) and in adults ≥65 years^11 (Study 11, conducted in Europe). Based on analysis of the primary pre-specified comparison of serotype specific anti-capsular polysaccharide IgG GMCs, noninferiority was met for all serotypes in adults 50–59 years of age and for 12 of 13 serotypes in adults ≥65years of age.

15 REFERENCES

ClinicalTrials.gov identifiers for studies included below:

1. Study 1 NCT00205803
2. Study 2 NCT00373958
3. Study 3 NCT00444457
4. Study 4 NCT00452452
5. Study 5 NCT00761631
6. Study 6 NCT00427895
7. Study 7 NCT00546572
8. Study 8 NCT00574548
9. Study 9 NCT00500266
10. Study 10 NCT00521586
11. Study 11 NCT00492557
12. Study 12 NCT00744263
13. Study 13 NCT02124161

16 HOW SUPPLIED/STORAGE AND HANDLING

Product: 50090-1944

NDC: 50090-1944-0 .5 mL in a SYRINGE / 1 in a POUCH

17 PATIENT COUNSELING INFORMATION

Prior to administration of this vaccine, inform the individual, parent, guardian, or other responsible adult of the following:

- The potential benefits and risks of immunization with Prevnar 13 [see Warnings and Precautions (5) and Adverse Reactions (6)].
- The importance of completing the immunization series unless contraindicated.
- Any suspected adverse reactions should be reported to their healthcare professional.

Provide the Vaccine Information Statements, which are available free of charge at the Centers for Disease Control and Prevention (CDC) website (www.cdc.gov/vaccines).

This product's label may have been updated. For current full prescribing information, please visit www.pfizer.com.

US Govt. License No. 3

LAB-0469-18.0
CPT Code 90670